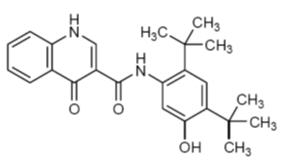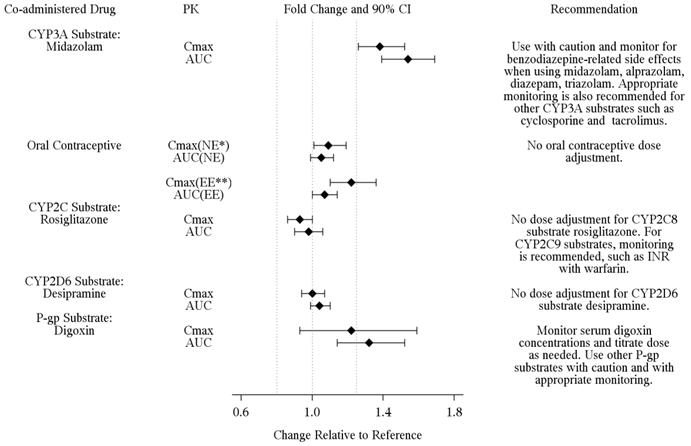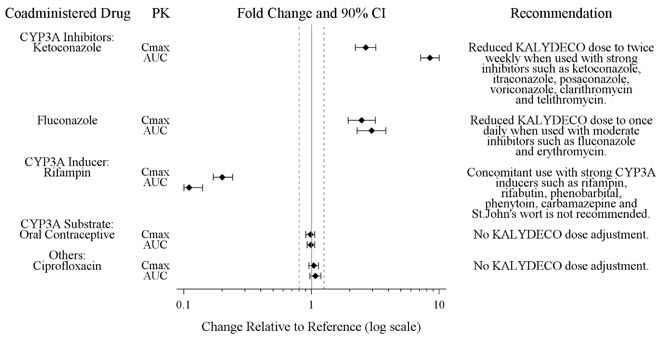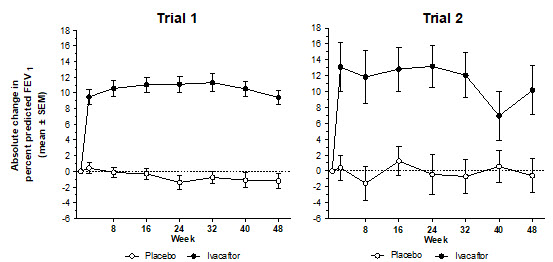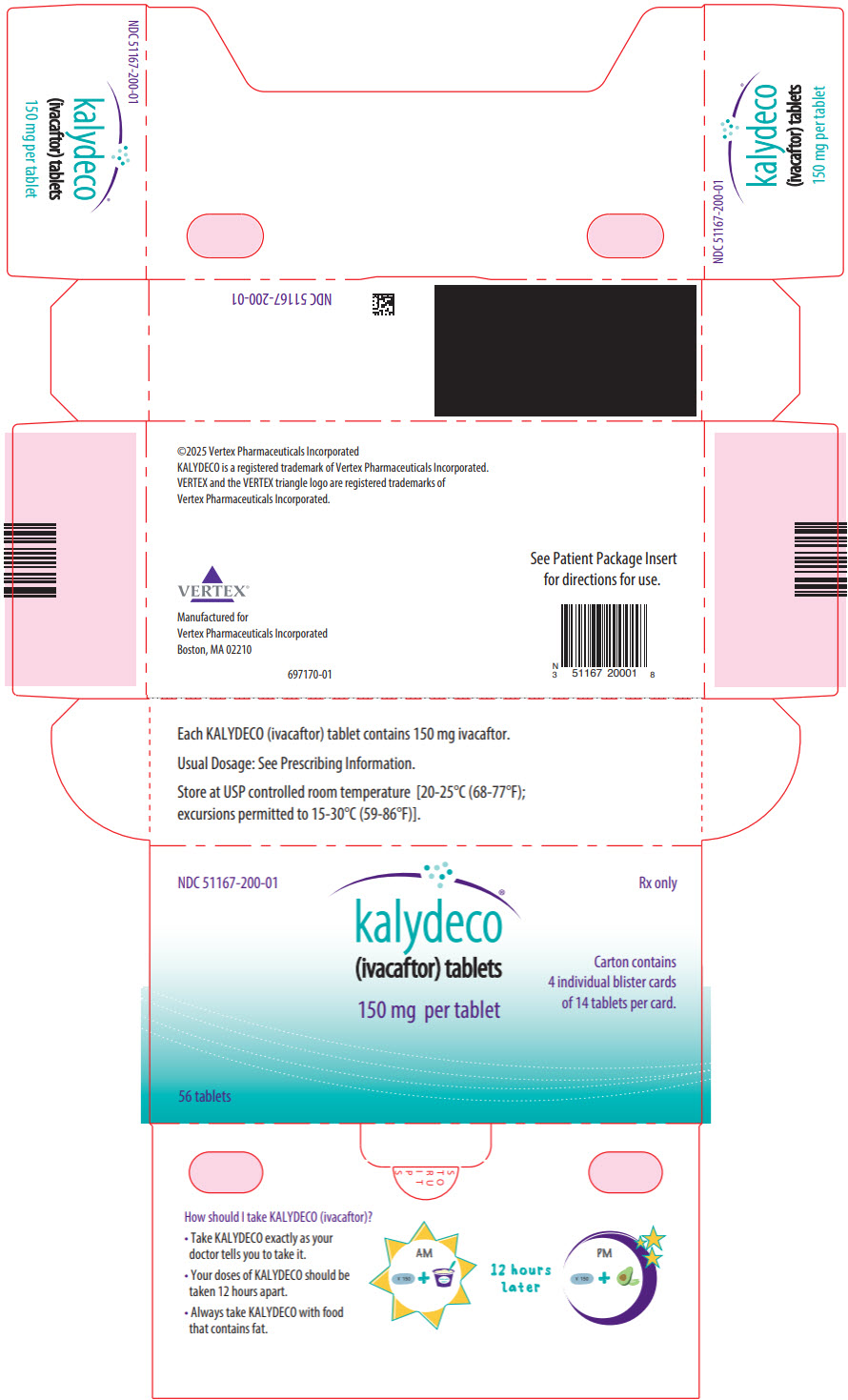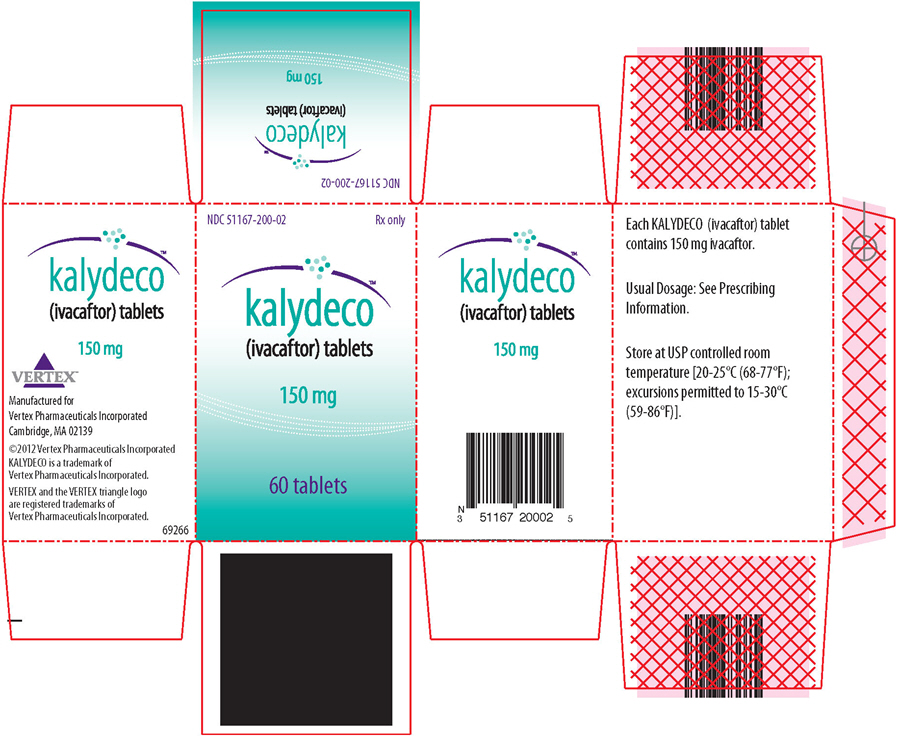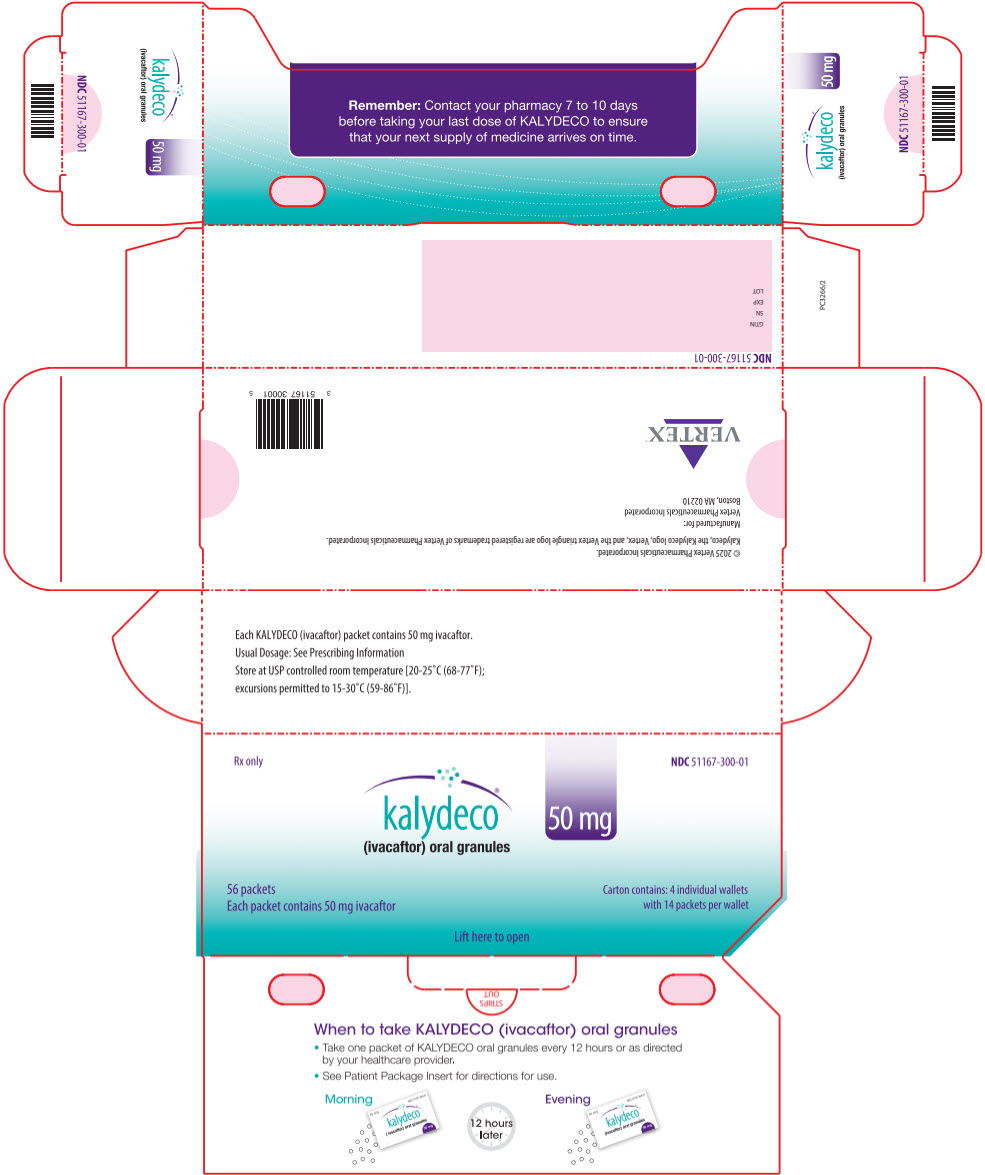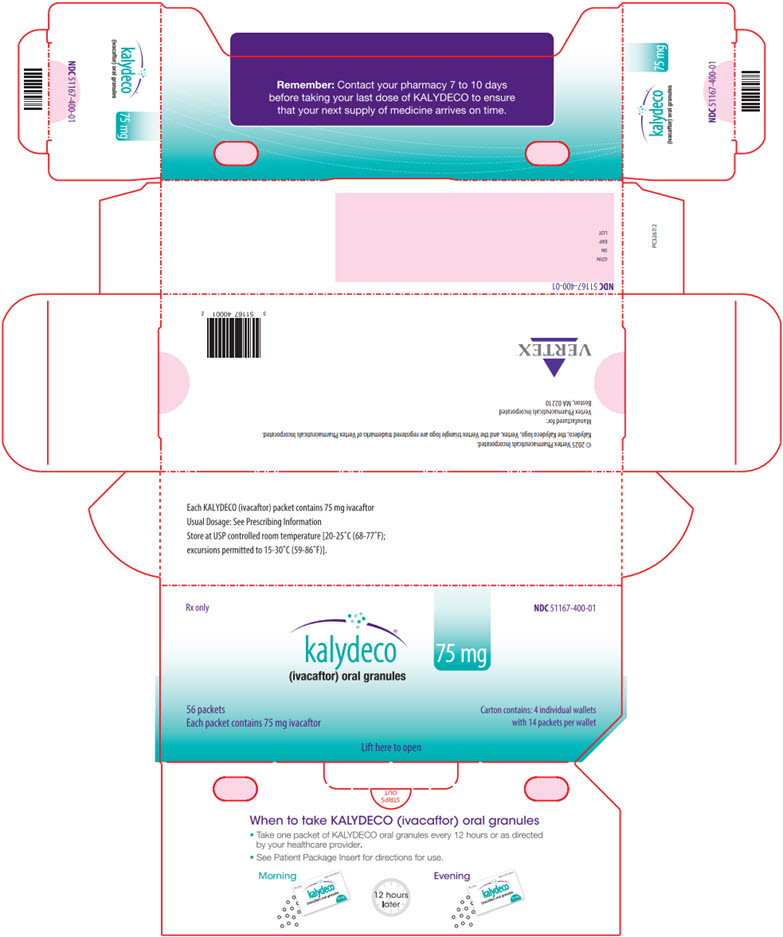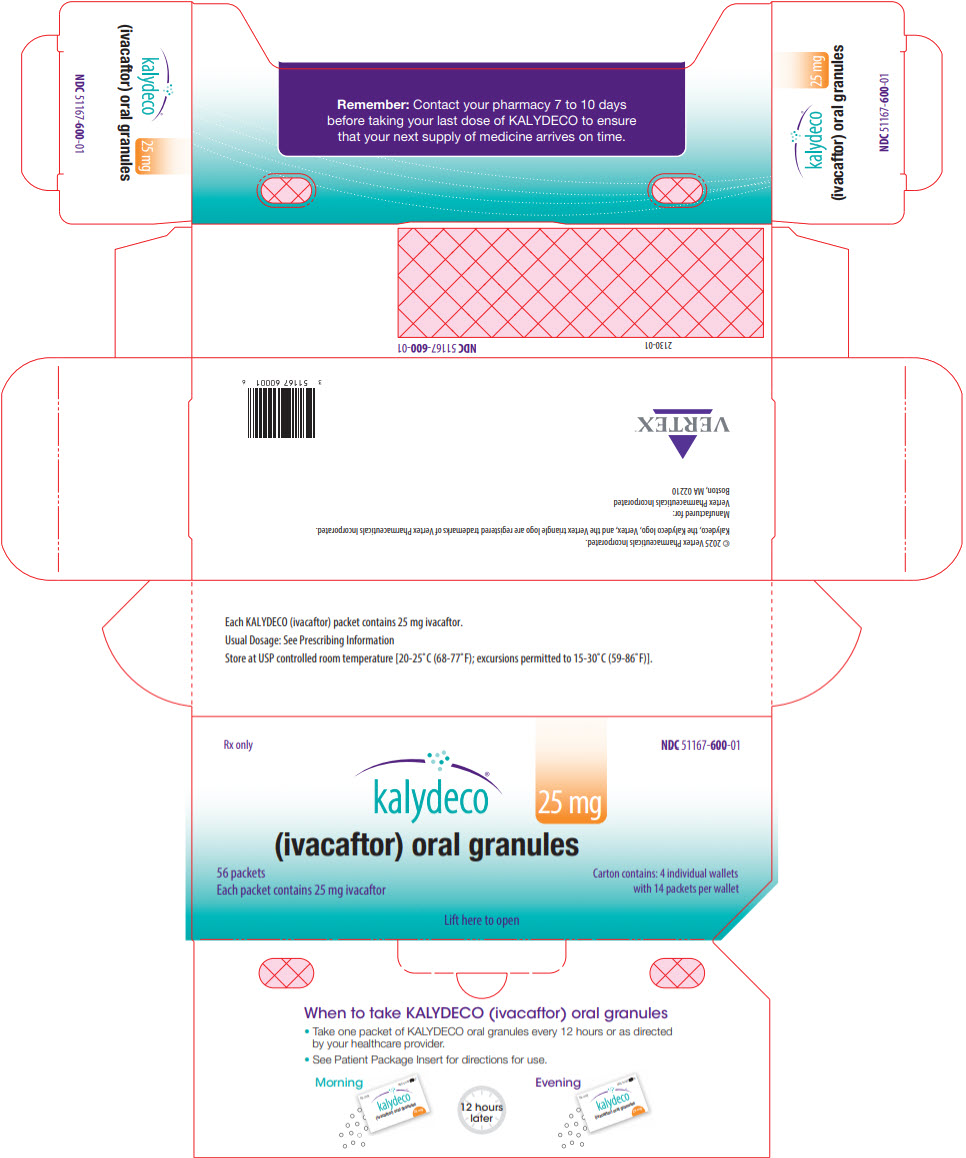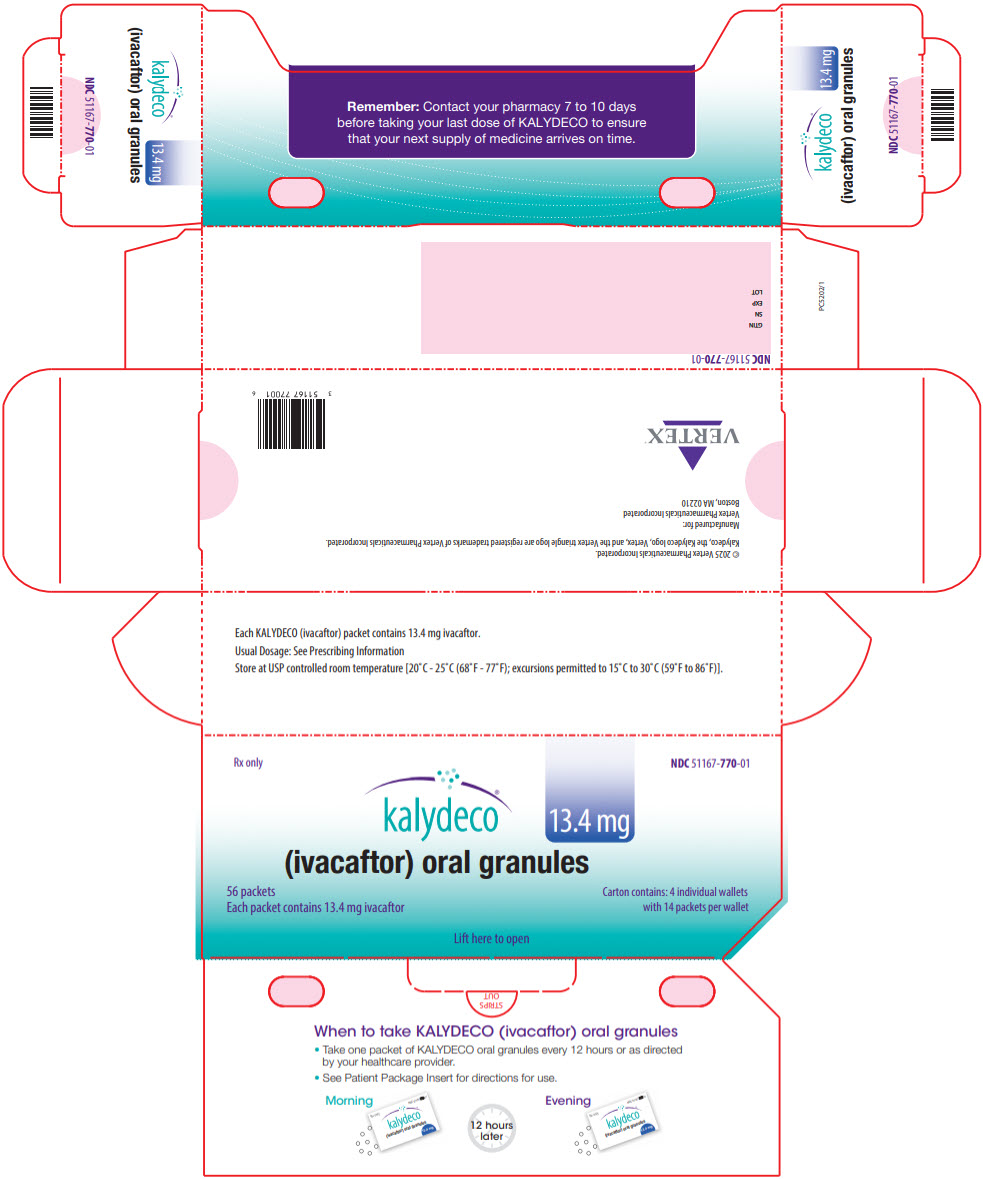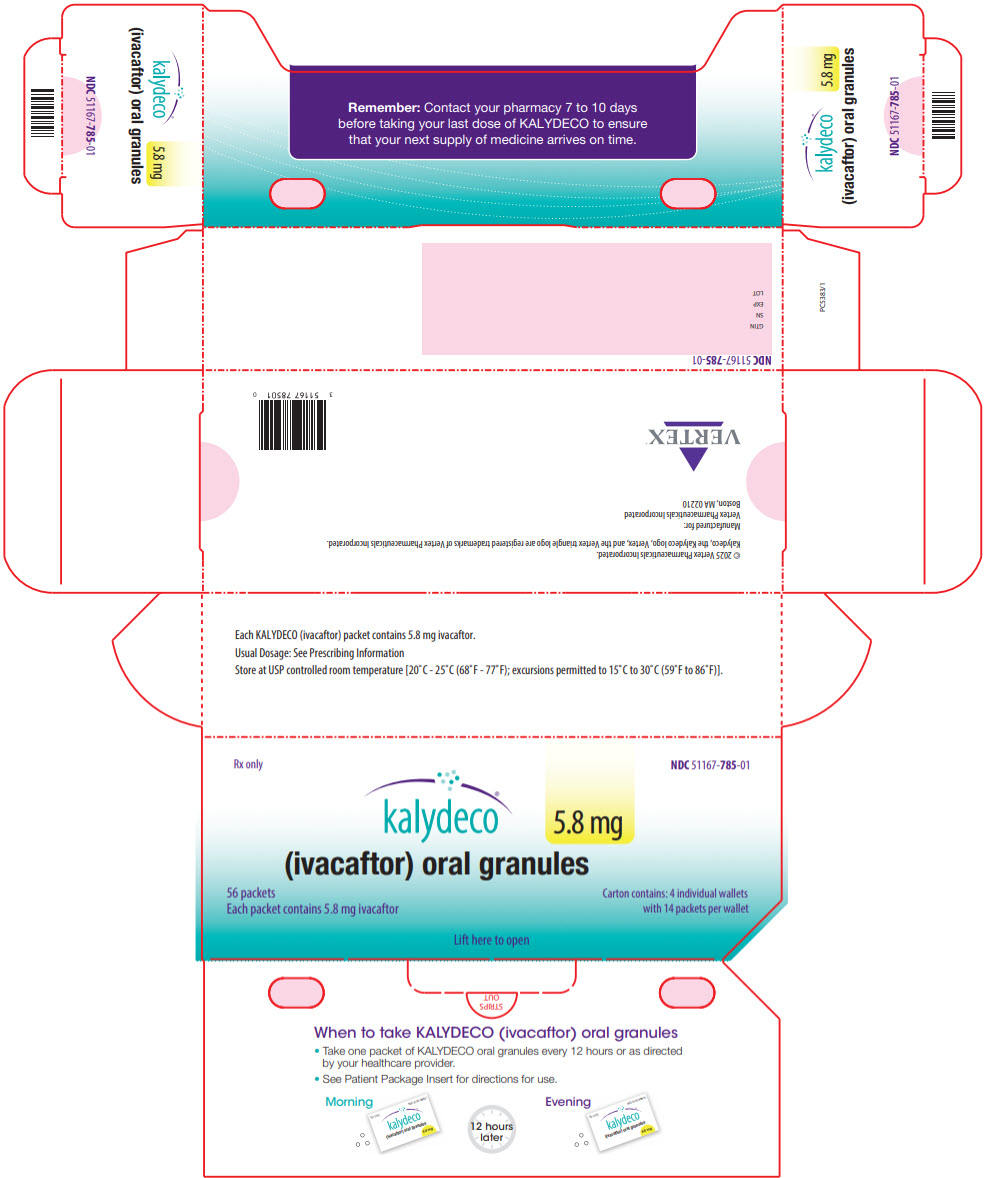 DRUG LABEL: Kalydeco
NDC: 51167-200 | Form: TABLET, FILM COATED
Manufacturer: Vertex Pharmaceuticals Incorporated
Category: prescription | Type: HUMAN PRESCRIPTION DRUG LABEL
Date: 20251210

ACTIVE INGREDIENTS: ivacaftor 150 mg/1 1
INACTIVE INGREDIENTS: SILICON DIOXIDE; CROSCARMELLOSE SODIUM; HYPROMELLOSE ACETATE SUCCINATE 06081224 (3 MPA.S); LACTOSE MONOHYDRATE; MAGNESIUM STEARATE; MICROCRYSTALLINE CELLULOSE; SODIUM LAURYL SULFATE; CARNAUBA WAX; FD&C Blue No. 2; POLYETHYLENE GLYCOL 3350; POLYVINYL ALCOHOL, UNSPECIFIED; TALC; TITANIUM DIOXIDE; AMMONIA; FERROSOFERRIC OXIDE; PROPYLENE GLYCOL; SHELLAC

HIGHLIGHTS OF PRESCRIBING INFORMATION

These highlights do not include all the information needed to use KALYDECO safely and effectively. See full prescribing information for KALYDECO.
KALYDECO® (ivacaftor) tablets, for oral use
KALYDECO® (ivacaftor) oral granules
Initial U.S. Approval: 2012

RECENT MAJOR CHANGES

Warnings and Precautions, Intracranial Hypertension (5.3) | 09/2025

1 INDICATIONS AND USAGE

KALYDECO is a cystic fibrosis transmembrane conductance regulator (CFTR) potentiator indicated for the treatment of cystic fibrosis (CF) in patients aged 1 month and older who have at least one mutation in the CFTR gene that is responsive to ivacaftor based on clinical and/or in vitro assay data. (12.1, 14)

If the patient's genotype is unknown, an FDA-cleared CF mutation test should be used to detect the presence of a CFTR mutation followed by verification with bi-directional sequencing when recommended by the mutation test instructions for use. (1)

2 DOSAGE AND ADMINISTRATION

Age | Weight | Dosage | Administration
1 month to less than 2 months | 3 kg or greater | One 5.8 mg packet every 12 hours | Mixed with one teaspoon (5 mL) of soft food or liquid and administered orally with fat-containing food
2 months to less than 4 months | 3 kg or greater | One 13.4 mg packet every 12 hours | Mixed with one teaspoon (5 mL) of soft food or liquid and administered orally with fat-containing food
4 months to less than 6 months | 5 kg or greater | One 25 mg packet every 12 hours | Mixed with one teaspoon (5 mL) of soft food or liquid and administered orally with fat-containing food
6 months to less than 6 years | 5 kg to less than 7 kg | One 25 mg packet every 12 hours | Mixed with one teaspoon (5 mL) of soft food or liquid and administered orally with fat-containing food
6 months to less than 6 years | 7 kg to less than 14 kg | One 50 mg packet every 12 hours | Mixed with one teaspoon (5 mL) of soft food or liquid and administered orally with fat-containing food
6 months to less than 6 years | 14 kg or greater | One 75 mg packet every 12 hours | Mixed with one teaspoon (5 mL) of soft food or liquid and administered orally with fat-containing food
6 years and older | - | One 150 mg tablet every 12 hours | Taken orally with fat-containing food

- See full prescribing information for the recommended dosage in patients aged 6 months and older with moderate or severe hepatic impairment. (2.3, 8.6)
- See full prescribing information for dosage modifications due to drug interactions with KALYDECO. (2.4, 7.1)
- Not recommended in pediatric patients less than 1 month of age. (2.2, 8.4)
- Not recommended in patients 1 month to less than 6 months of age with any level of hepatic impairment and/or taking concomitant moderate or strong CYP3A inhibitors. (2.3, 2.4, 8.6)

3 DOSAGE FORMS AND STRENGTHS

- Tablets: 150 mg. (3)
- Oral granules: Unit-dose packets of 5.8 mg, 13.4 mg, 25 mg, 50 mg, and 75 mg. (3)

4 CONTRAINDICATIONS

- None (4)

5 WARNINGS AND PRECAUTIONS

- Elevated transaminases (ALT or AST): Transaminases (ALT and AST) should be assessed prior to initiating KALYDECO, every 3 months during the first year of treatment, and annually thereafter. In patients with a history of transaminase elevations, more frequent monitoring of liver function tests should be considered. Patients who develop increased transaminase levels should be closely monitored until the abnormalities resolve. Interrupt dosing in patients with ALT or AST of greater than 5 times the upper limit of normal (ULN). Following resolution of transaminase elevations, consider the benefits and risks of resuming KALYDECO dosing. (5.1, 6)
- Hypersensitivity reactions: Anaphylaxis has been reported with KALYDECO in the postmarketing setting. Initiate appropriate therapy in the event of a hypersensitivity reaction. (5.2)
- Intracranial hypertension: Intracranial hypertension (IH) has been reported in the postmarketing setting with use of drugs containing the same or similar active ingredients as KALYDECO. If an unusual headache or visual disturbances occur during treatment, and IH is suspected, interrupt KALYDECO and refer for prompt medical evaluation. (5.3)
- Use with CYP3A inducers: Concomitant use with strong CYP3A inducers (e.g., rifampin, St. John's wort) substantially decreases exposure of ivacaftor, which may diminish effectiveness. Therefore, co-administration is not recommended. (5.4, 7.2, 12.3)
- Cataracts: Non-congenital lens opacities/cataracts have been reported in pediatric patients treated with KALYDECO. Baseline and follow-up examinations are recommended in pediatric patients initiating KALYDECO treatment. (5.5)

6 ADVERSE REACTIONS

The most common adverse drug reactions to KALYDECO (≥8% of patients with CF who have a G551D mutation in the CFTR gene) were headache, oropharyngeal pain, upper respiratory tract infection, nasal congestion, abdominal pain, nasopharyngitis, diarrhea, rash, nausea, and dizziness. (6.1)

To report SUSPECTED ADVERSE REACTIONS, contact Vertex Pharmaceuticals Incorporated at 1-877-634-8789 or FDA at 1-800-FDA-1088 or www.fda.gov/medwatch.

7 DRUG INTERACTIONS

CYP3A inhibitors: Reduce KALYDECO dosage in patients aged 6 months and older when co-administered with strong CYP3A inhibitors (e.g., ketoconazole) or moderate CYP3A inhibitors (e.g., fluconazole). KALYDECO is not recommended in patients aged 1 month to less than 6 months when co-administered with strong or moderate CYP3A inhibitors. Avoid food or drink containing grapefruit. (2.4, 7.1)

FULL PRESCRIBING INFORMATION

1 INDICATIONS AND USAGE

KALYDECO is indicated for the treatment of cystic fibrosis (CF) in patients aged 1 month and older who have at least one mutation in the CFTR gene that is responsive to ivacaftor potentiation based on clinical and/or in vitro assay data [see Clinical Pharmacology (12.1) and Clinical Studies (14)].

If the patient's genotype is unknown, an FDA-cleared CF mutation test should be used to detect the presence of a CFTR mutation followed by verification with bi-directional sequencing when recommended by the mutation test instructions for use.

2 DOSAGE AND ADMINISTRATION

2.1 Recommended Dosage in Adults and Pediatric Patients Aged 6 Years and Older

The recommended dosage of KALYDECO for adults and pediatric patients aged 6 years and older is 150 mg orally every 12 hours (300 mg total daily dose) with fat-containing food [see Dosage and Administration (2.5)].

2.2 Recommended Dosage in Pediatric Patients Aged 1 Month to Less than 6 Years

The recommended dosage of KALYDECO (oral granules) for pediatric patients aged 1 month to less than 6 years is weight-based provided in Table 1. Take KALYDECO orally with fat-containing food [see Dosage and Administration (2.5)].

Table 1: Recommended Dosage of KALYDECO Oral Granules by Body Weight in Pediatric Patients Aged 1 Month to Less than 6 Years
Age | Body Weight (kg) | KALYDECO Dosage
1 month to less than 2 months [KALYDECO is not recommended for use in pediatric patients under 1 month of age.] [Use of KALYDECO in pediatric patients aged 1 to less than 6 months born at a gestational age less than 37 weeks has not been evaluated.] | 3 kg or greater | One packet (containing 5.8 mg ivacaftor) every 12 hours
2 months to less than 4 months | 3 kg or greater | One packet (containing 13.4 mg ivacaftor) every 12 hours
4 months to less than 6 months | 5 kg or greater | One packet (containing 25 mg ivacaftor) every 12 hours
6 months to less than 6 years of age | 5 kg to less than 7 kg | One packet (containing 25 mg ivacaftor) every 12 hours
6 months to less than 6 years of age | 7 kg to less than 14 kg | One packet (containing 50 mg ivacaftor) every 12 hours
6 months to less than 6 years of age | 14 kg or greater | One packet (containing 75 mg ivacaftor) every 12 hours

2.3 Recommended Dosage for Patients with Hepatic Impairment

KALYDECO is not recommended in patients less than 6 months of age with any level of hepatic impairment. The following is the recommended dosage of KALYDECO taken with fat-containing food [see Dosage and Administration (2.5)] for patients aged 6 months and older with hepatic impairment:

- Mild Hepatic Impairment (Child-Pugh Class A):
  - Less than 6 months of age: KALYDECO is not recommended.
  - No dosage adjustment is necessary for patients aged 6 months or older [see Clinical Pharmacology (12.3)].
- Moderate Hepatic Impairment (Child-Pugh Class B):
  - Less than 6 months of age: KALYDECO is not recommended.
  - 6 months to less than 6 years of age: one packet (containing 25 mg, 50 mg, or 75 mg ivacaftor) of oral granules once daily based on dosing recommended for age and weight in Table 1 [see Dosage and Administration (2.2)].
  - 6 years of age and older: 150 mg orally once daily.
- Severe Hepatic Impairment (Child-Pugh Class C): Should not be used in patients less than 6 months of age. In patients aged 6 months and older should be used with caution. KALYDECO has not been studied in patients with severe hepatic impairment (Child-Pugh Class C), but exposure is expected to be higher than in patients with moderate hepatic impairment. Therefore, use with caution at a reduced dosage, in patients aged 6 months or older with severe hepatic impairment after weighing the risks and benefits of treatment [see Dosage and Administration (2.1, 2.2) and Clinical Pharmacology (12.3)].
  - Less than 6 months of age: KALYDECO is not recommended.
  - 6 months to less than 6 years of age: one packet (containing 25 mg, 50 mg, or 75 mg ivacaftor) of oral granules once daily or less frequently based on dosing recommended for age and weight in Table 1 [see Dosage and Administration (2.2)].
  - 6 years of age and older: 150 mg orally once daily or less frequently.

2.4 Dosage Modification for Patients Taking Drugs that are CYP3A Inhibitors

Concomitant use of moderate or strong CYP3A inhibitors is not recommended in patients below 6 months of age. Food or drink containing grapefruit should be avoided [see Drug Interactions (7.1) and Clinical Pharmacology (12.3)]. Take KALYDECO with fat-containing food [see Dosage and Administration (2.5)].

Dosage modification for patients 6 months of age and older taking CYP3A inhibitors:

- Moderate CYP3A inhibitors:
  - Less than 6 months of age: KALYDECO is not recommended.
  - 6 months to less than 6 years of age: one packet (containing 25 mg, 50 mg, or 75 mg ivacaftor) of oral granules once daily based on dosing recommended for age and weight in Table 1 [see Dosage and Administration (2.2)].
  - 6 years of age and older: 150 mg orally once daily.
- Strong CYP3A inhibitors:
  - Less than 6 months of age: KALYDECO is not recommended.
  - 6 months to less than 6 years of age: one packet (containing 25 mg, 50 mg, or 75 mg ivacaftor) of oral granules twice a week based on dosing recommended for age and weight in Table 1 [see Dosage and Administration (2.2)].
  - 6 years of age and older: 150 mg orally twice weekly.

2.5 Administration Information

Administer KALYDECO tablets or oral granules with fat-containing food. Examples include eggs, butter, peanut butter, cheese pizza, whole-milk dairy products (such as whole milk, cheese, yogurt, breast milk, or infant formula), etc. [see Clinical Pharmacology (12.3)].

Instruction for Administration of Tablets

Swallow tablets whole.

Instruction for Administration of Oral Granules

Administer each dose of KALYDECO oral granules immediately before or after ingestion of fat-containing food. Mix the entire contents of each packet of oral granules with one teaspoon (5 mL) of age-appropriate soft food or liquid that is at or below room temperature. Some examples of soft foods or liquids may include puréed fruits or vegetables, yogurt, applesauce, water, breast milk, infant formula, milk, or juice. Food or liquid should be at or below room temperature. Once mixed, the product should be completely consumed within one hour.

3 DOSAGE FORMS AND STRENGTHS

Tablets: 150 mg, light blue, film-coated, oblong-shaped tablets, with the characters "V 150" on one side and plain on the other.

Oral granules: 5.8 mg, 13.4 mg, 25 mg, 50 mg, or 75 mg, white to off-white granules, in unit-dose packets.

4 CONTRAINDICATIONS

None.

5 WARNINGS AND PRECAUTIONS

5.1 Transaminase (ALT or AST) Elevations

Elevated transaminases have been reported in patients with CF receiving KALYDECO. ALT and AST should be assessed prior to initiating KALYDECO, every 3 months during the first year of treatment, and annually thereafter. For patients with a history of transaminase elevations, consider more frequent monitoring of liver function tests. Patients who develop increased transaminase levels should be closely monitored until the abnormalities resolve. Dosing should be interrupted in patients with ALT or AST of greater than 5 times the upper limit of normal (ULN). Following resolution of transaminase elevations, consider the benefits and risks of resuming KALYDECO [see Adverse Reactions (6) and Use in Specific Populations (8.6)].

5.2 Hypersensitivity Reactions, Including Anaphylaxis

Hypersensitivity reactions, including cases of anaphylaxis, have been reported in the postmarketing setting [see Adverse Reactions (6.2)]. If signs or symptoms of serious hypersensitivity reactions develop during treatment, discontinue KALYDECO and institute appropriate therapy. Consider the benefits and risks for the individual patient to determine whether to resume treatment with KALYDECO.

5.3 Intracranial Hypertension

Cases of intracranial hypertension (IH) have been reported in the postmarketing setting with the use of drugs containing the same or similar active ingredients as KALYDECO [see Adverse Reactions (6.2)]. Clinical manifestations of IH include headache, blurred vision, diplopia, and potential vision loss; papilledema can be found on fundoscopy. If an unusual headache or visual disturbances occur during treatment, and IH is suspected, interrupt KALYDECO and refer for prompt medical evaluation. Consider the benefits and risks for the individual patient to determine whether to resume treatment with KALYDECO. Patients should be monitored until IH resolution and for recurrence. Patients with elevated vitamin A levels may be at increased risk.

5.4 Concomitant Use with CYP3A Inducers

Use of KALYDECO with strong CYP3A inducers, such as rifampin, substantially decreases the exposure of ivacaftor, which may reduce the therapeutic effectiveness of KALYDECO. Therefore, co-administration of KALYDECO with strong CYP3A inducers (e.g., rifampin, St. John's wort) is not recommended [see Drug Interactions (7.2) and Clinical Pharmacology (12.3)].

5.5 Cataracts

Cases of non-congenital lens opacities/cataracts have been reported in pediatric patients treated with KALYDECO. Although other risk factors were present in some cases (such as corticosteroid use and/or exposure to radiation), a possible risk attributable to KALYDECO cannot be excluded. Baseline and follow-up ophthalmological examinations are recommended in pediatric patients initiating KALYDECO treatment.

6 ADVERSE REACTIONS

The following adverse reactions are discussed in greater detail in other sections of the labeling:

- Transaminase Elevations [see Warnings and Precautions (5.1)]
- Hypersensitivity Reactions, Including Anaphylaxis [see Warnings and Precautions (5.2)]
- Intracranial Hypertension [see Warnings and Precautions (5.3)]
- Cataracts [see Warnings and Precautions (5.5)]

6.1 Clinical Trials Experience

Because clinical trials are conducted under widely varying conditions, adverse reaction rates observed in the clinical trials of a drug cannot be directly compared to rates in the clinical trials of another drug and may not reflect the rates observed in clinical practice.

The overall safety profile of KALYDECO is based on pooled data from three placebo-controlled clinical trials conducted in 353 patients 6 years of age and older with CF who had a G551D mutation in the CFTR gene (Trials 1 and 2) or were homozygous for the F508del mutation (Trial 3). In addition, the following clinical trials have also been conducted [see Clinical Pharmacology (12) and Clinical Studies (14)]:

- An 8-week, crossover design trial (Trial 4) involving 39 patients between the ages of 6 and 57 years with a G1244E, G1349D, G178R, G551S, G970R, S1251N, S1255P, S549N, or S549R mutation in the CFTR gene.
- A 24-week, placebo-controlled trial (Trial 5) involving 69 patients between the ages of 6 and 68 years with an R117H mutation in the CFTR gene.
- A 24-week, open-label trial (Trial 6) in 34 patients 2 to less than 6 years of age. Patients eligible for Trial 6 were those with the G551D, G1244E, G1349D, G178R, G551S, G970R, S1251N, S1255P, S549N, or S549R mutation in the CFTR gene. Of 34 patients enrolled, 32 had the G551D mutation and 2 had the S549N mutation.
- An 8-week, crossover design trial (Trial 7) involving patients between the ages of 12 and 72 years who were heterozygous for the F508del mutation and a second CFTR mutation predicted to be responsive to ivacaftor. A total of 156 patients were randomized to and received KALYDECO.
- A 24-week open-label clinical trial in patients with CF aged less than 24 months (Trial 8) including a cohort of 19 patients aged 12 months to less than 24 months, a cohort of 11 patients aged 6 months to less than 12 months, a cohort of 6 patients aged 4 months to less than 6 months, and a cohort of 7 patients aged 1 month to less than 4 months. Patients with a gating mutation or R117H mutation were eligible for the first three cohorts of this study. Patients with any ivacaftor-responsive mutation were eligible for the cohort aged 1 to less than 4 months.

Of the 353 patients included in the pooled analyses of patients with CF who had either a G551D mutation or were homozygous for the F508del mutation in the CFTR gene, 50% of patients were female and 97% were Caucasian; 221 received KALYDECO, and 132 received placebo for 16 to 48 weeks.

The proportion of patients who prematurely discontinued study drug due to adverse reactions was 2% for KALYDECO-treated patients and 5% for placebo-treated patients. Serious adverse reactions, whether considered drug-related or not by the investigators, that occurred more frequently in KALYDECO-treated patients, included abdominal pain, increased hepatic enzymes, and hypoglycemia.

The most common adverse reactions in the 221 patients treated with KALYDECO were headache (17%), upper respiratory tract infection (16%), nasal congestion (16%), nausea (10%), rash (10%), rhinitis (6%), dizziness (5%), arthralgia (5%), and bacteria in sputum (5%).

The incidence of adverse reactions below is based upon two double-blind, placebo-controlled, 48-week clinical trials (Trials 1 and 2) in a total of 213 patients with CF ages 6 to 53 who have a G551D mutation in the CFTR gene and who were treated with KALYDECO 150 mg orally or placebo twice daily. Table 2 shows adverse reactions occurring in ≥8% of KALYDECO-treated patients with CF who have a G551D mutation in the CFTR gene that also occurred at a higher rate than in the placebo-treated patients in the two double-blind, placebo-controlled trials.

Table 2: Incidence of Adverse Drug Reactions in ≥8% of KALYDECO-Treated Patients with a G551D Mutation in the CFTR Gene and Greater than Placebo in 2 Placebo-Controlled Phase 3 Clinical Trials of 48 Weeks Duration
Adverse Reaction (Preferred Term) | Incidence: Pooled 48-Week Trials
Adverse Reaction (Preferred Term) | KALYDECO N=109 n (%) | Placebo N=104 n (%)
Headache | 26 (24) | 17 (16)
Oropharyngeal pain | 24 (22) | 19 (18)
Upper respiratory tract infection | 24 (22) | 14 (14)
Nasal congestion | 22 (20) | 16 (15)
Abdominal pain | 17 (16) | 13 (13)
Nasopharyngitis | 16 (15) | 12 (12)
Diarrhea | 14 (13) | 10 (10)
Rash | 14 (13) | 7 (7)
Nausea | 13 (12) | 11 (11)
Dizziness | 10 (9) | 1 (1)

Adverse reactions in the 48-week clinical trials that occurred in the KALYDECO group at a frequency of 4 to 7% where rates exceeded that in the placebo group include:

Infections and infestations: rhinitis
Investigations: aspartate aminotransferase increased, bacteria in sputum, blood glucose increased, hepatic enzyme increased
Musculoskeletal and connective tissue disorders: arthralgia, musculoskeletal chest pain, myalgia
Nervous system disorders: sinus headache
Respiratory, thoracic and mediastinal disorders: pharyngeal erythema, pleuritic pain, sinus congestion, wheezing
Skin and subcutaneous tissue disorders: acne

The safety profile for the CF patients enrolled in the other clinical trials (Trials 3-8) was similar to that observed in the 48-week, placebo-controlled trials (Trials 1 and 2).

Laboratory Abnormalities

Transaminase Elevations: In Trials 1, 2, and 3 the incidence of maximum transaminase (ALT or AST) >8, >5, or >3 × ULN was 2%, 2%, and 6% in KALYDECO-treated patients and 2%, 2%, and 8% in placebo-treated patients, respectively. Two patients (2%) on placebo and 1 patient (0.5%) on KALYDECO permanently discontinued treatment for elevated transaminases, all >8 × ULN. Two patients treated with KALYDECO were reported to have serious adverse reactions of elevated liver transaminases compared to none on placebo. Transaminase elevations were more common in patients with a history of transaminase elevations [see Warnings and Precautions (5.1)].

During the 24-week, open-label, clinical trial in 34 patients ages 2 to less than 6 years (Trial 6), where patients received either 50 mg (less than 14 kg) or 75 mg (14 kg or greater) ivacaftor granules twice daily, the incidence of patients experiencing transaminase elevations (ALT or AST) >3 × ULN was 14.7% (5/34). All 5 patients had maximum ALT or AST levels >8 × ULN, which returned to baseline levels following interruption of KALYDECO dosing. Transaminase elevations were more common in patients who had abnormal transaminases at baseline. KALYDECO was permanently discontinued in one patient [see Warnings and Precautions (5.1)].

During the 24-week, open-label, clinical trial in patients aged less than 24 months (Trial 8), the incidence of patients experiencing transaminase elevations (ALT or AST) >3, >5, and >8 × ULN in the cohort of patients aged 12 months to less than 24 months (N=19) was 27.8% (5/18), 11.1% (2/18) and 11.1% (2/18), respectively. In the cohort of patients aged 6 months to less than 12 months (N=11) one patient (9.1%) had elevated ALT of >3 to ≤5 × ULN. In the cohort of patients aged 4 months to less than 6 months (N=6), no patients had elevated ALT or AST (>3× ULN). In the cohort of patients aged 1 month to less than 4 months (N=7), 1 patient (14.3%) had maximum ALT or AST >3 × ULN (ALT >8 × ULN and AST of >3 to ≤5 × ULN); the patient discontinued ivacaftor treatment [see Warnings and Precautions (5.1)].

6.2 Postmarketing Experience

Postmarketing Adverse Reactions with KALYDECO

The following adverse reactions have been identified during post approval use of KALYDECO. Because these reactions are reported voluntarily from a population of uncertain size, it is not always possible to reliably estimate their frequency or establish a causal relationship to drug exposure.

Immune System Disorders: anaphylaxis

Postmarketing Adverse Reactions with Other Drugs Containing the Same or Similar Active Ingredients as KALYDECO

The following adverse reactions have been identified during post approval use of drugs containing the same or similar active ingredients as KALYDECO. Because these reactions are reported voluntarily from a population of uncertain size, it is not always possible to reliably estimate their frequency or establish a causal relationship to drug exposure.

Nervous System Disorders: intracranial hypertension

7 DRUG INTERACTIONS

Potential for other drugs to affect ivacaftor

7.1 Inhibitors of CYP3A

Ivacaftor is a sensitive CYP3A substrate. Co-administration with ketoconazole, a strong CYP3A inhibitor, significantly increased ivacaftor exposure [measured as area under the curve (AUC)] by 8.5-fold. Based on simulations of these results, a reduction of the KALYDECO dosage is recommended for patients aged 6 months and older taking concomitant strong CYP3A inhibitors, such as ketoconazole, itraconazole, posaconazole, voriconazole, telithromycin, and clarithromycin. KALYDECO is not recommended for patients less than 6 months of age taking strong CYP3A inhibitors [see Dosage and Administration (2.4) and Clinical Pharmacology (12.3)].

Co-administration with fluconazole, a moderate inhibitor of CYP3A, increased ivacaftor exposure by 3-fold. Therefore, a reduction of the KALYDECO dosage is recommended for patients aged 6 months and older taking concomitant moderate CYP3A inhibitors, such as fluconazole and erythromycin. KALYDECO is not recommended for patients less than 6 months of age taking moderate CYP3A inhibitors [see Dosage and Administration (2.4) and Clinical Pharmacology (12.3)].

Co-administration of KALYDECO with grapefruit juice, which contains one or more components that moderately inhibit CYP3A, may increase exposure of ivacaftor. Therefore, avoid food or drink containing grapefruit during treatment with KALYDECO [see Clinical Pharmacology (12.3)].

7.2 Inducers of CYP3A

Co-administration with rifampin, a strong CYP3A inducer, significantly decreased ivacaftor exposure (AUC) by approximately 9-fold. Therefore, co-administration with strong CYP3A inducers, such as rifampin, rifabutin, phenobarbital, carbamazepine, phenytoin, and St. John's wort is not recommended [see Warnings and Precautions (5.4) and Clinical Pharmacology (12.3)].

7.3 Ciprofloxacin

Co-administration of KALYDECO with ciprofloxacin had no effect on the exposure of ivacaftor. Therefore, no dosage adjustment is necessary during concomitant administration of KALYDECO with ciprofloxacin [see Clinical Pharmacology (12.3)].

Potential for ivacaftor to affect other drugs

7.4 CYP2C9 Substrates

Ivacaftor may inhibit CYP2C9; therefore, monitoring of the international normalized ratio (INR) during co-administration of KALYDECO with warfarin is recommended. Other therapeutic products for which exposure may be increased by KALYDECO include glimepiride and glipizide; these therapeutic products should be used with caution [see Clinical Pharmacology (12.3)].

7.5 CYP3A and/or P-gp Substrates

Ivacaftor and its M1 metabolite have the potential to inhibit CYP3A and P-gp. Co-administration with oral midazolam, a sensitive CYP3A substrate, increased midazolam exposure 1.5-fold, consistent with weak inhibition of CYP3A by ivacaftor. Co-administration with digoxin, a sensitive P-gp substrate, increased digoxin exposure by 1.3-fold, consistent with weak inhibition of P-gp by ivacaftor. Administration of KALYDECO may increase systemic exposure of drugs that are substrates of CYP3A and/or P-gp, which may increase or prolong their therapeutic effect and adverse events. Therefore, caution and appropriate monitoring are recommended when co-administering KALYDECO with sensitive CYP3A and/or P-gp substrates, such as digoxin, cyclosporine, and tacrolimus [see Clinical Pharmacology (12.3)].

8 USE IN SPECIFIC POPULATIONS

8.1 Pregnancy

Risk Summary

There are limited and incomplete human data from clinical trials and postmarketing reports on use of KALYDECO in pregnant women. In animal reproduction studies, oral administration of ivacaftor to pregnant rats and rabbits during organogenesis demonstrated no teratogenicity or adverse effects on fetal development at doses that produced maternal exposures up to approximately 5 (rats) and 11 (rabbits) times the exposure at the maximum recommended human dose (MRHD). No adverse developmental effects were observed after oral administration of ivacaftor to pregnant rats from organogenesis through lactation at doses that produced maternal exposures approximately 3 times the exposures at the MRHD, respectively (see Data).

The background risk of major birth defects and miscarriage for the indicated population is unknown. In the U.S. general population, the estimated background risk of major birth defects is 2% to 4% and miscarriage is 15% to 20% in clinically recognized pregnancies.

Data

Animal Data

In an embryo-fetal development study, pregnant rats were administered ivacaftor at oral doses of 50, 100, or 200 mg/kg/day during the period of organogenesis from gestation days 7-17. Ivacaftor did not affect fetal survival at exposures up to 5 times the MRHD (based on summed AUCs for ivacaftor and its metabolites at maternal oral doses up to 200 mg/kg/day). Maternal toxicity was observed at 100 and 200 mg/kg/day (3 and 5 times the exposure at the MRHD) and was associated with a decrease in fetal body weights at a maternal dose of 200 mg/kg/day (5 times the MRHD). In an EFD study, pregnant rabbits were administered ivacaftor at oral doses of 25, 50, or 100 mg/kg/day during the period of organogenesis from gestation days 7-19. Ivacaftor did not affect fetal development or survival at exposures up to 11 times the MRHD (on an ivacaftor AUC basis at maternal oral doses up to 100 mg/kg/day). Maternal toxicity (i.e., death, decreased food consumption, decreased mean body weight and body weight gain, decreased clinical condition, abortions) was observed at doses greater than or equal to 50 mg/kg/day (approximately 5 times the MRHD). In a pre- and post-natal development study, pregnant female rats were administered ivacaftor at oral doses of 50, 100, or 200 mg/kg/day from gestation day 7 through lactation day 20. Ivacaftor had no effects on delivery or growth and development of offspring at exposures up to 3 times the MRHD (based on summed AUCs for ivacaftor and its metabolites at maternal oral doses up to 100 mg/kg/day). Decreased fetal body weights were observed at a maternally toxic dose that produced exposures 5 times the MRHD (based on summed AUCs for ivacaftor and its metabolites at a maternal oral dose of 200 mg/kg/day). Placental transfer of ivacaftor was observed in pregnant rats and rabbits.

8.2 Lactation

Risk Summary

There is no information regarding the presence of ivacaftor in human milk, the effects on the breastfed infant, or the effects on milk production. Ivacaftor is excreted into the milk of lactating rats; however, due to species-specific differences in lactation physiology, animal lactation data may not reliably predict levels in human milk (see Data). The developmental and health benefits of breastfeeding should be considered along with the mother's clinical need for KALYDECO, and any potential adverse effects on the breastfed child from KALYDECO or from the underlying maternal condition.

Data

Lacteal excretion of ivacaftor in rats was demonstrated following a single oral dose (100 mg/kg) of ^14C-ivacaftor administered 9 to 10 days postpartum to lactating mothers (dams). Exposure (AUC0-24h) values for ivacaftor in milk were approximately 1.5 times higher than plasma levels.

8.4 Pediatric Use

The safety and effectiveness of KALYDECO for the treatment of CF have been established in pediatric patients 1 month to 17 years of age who have at least one mutation in the CFTR gene that is responsive to ivacaftor potentiation based on clinical and/or in vitro assay data [see Clinical Pharmacology (12.1) and Clinical Studies (14)].

The use of KALYDECO for this indication is supported by evidence from placebo-controlled clinical trials in the following pediatric patients with CF:

- 12 to 17 years of age who are heterozygous for the F508del mutation and a second mutation predicted to be responsive to ivacaftor [see Adverse Reactions (6) and Clinical Studies (14)].
- 6 to 17 years of age with a G551D, G1244E, G1349D, G178R, G551S, S1251N, S1255P, S549N, S549R, or R117H mutation in the CFTR gene [see Adverse Reactions (6) and Clinical Studies (14)].
- The effectiveness of KALYDECO in patients aged 2 to less than 6 years was extrapolated from patients 6 years of age and older with support from population pharmacokinetic analyses showing similar drug exposure levels in adults and pediatric patients 2 to less than 6 years of age [see Clinical Pharmacology (12.3)]. Safety of KALYDECO in this population was derived from a 24-week, open-label clinical trial in 34 patients ages 2 to less than 6 years (mean age 3 years) administered either 50 mg or 75 mg of ivacaftor granules twice daily (Trial 6). The type and frequency of adverse reactions in this trial were similar to those in patients aged 6 years and older. Transaminase elevations were more common in patients who had abnormal transaminases at baseline [see Warnings and Precautions (5.1) and Adverse Reactions (6.1)].
- The effectiveness of KALYDECO in patients aged 1 month to less than 24 months was extrapolated from patients 6 years of age and older with support from population pharmacokinetic analyses showing that the exposure of ivacaftor in pediatric patients 1 month to less than 24 months of age is within the range of exposure in adults and pediatric patients 6 years of age and older [see Clinical Pharmacology (12.3)]. Safety of KALYDECO in this population was derived from a cohort of 7 patients aged 1 month to less than 4 months (mean age 1.9 months at baseline), a cohort of 6 patients aged 4 months to less than 6 months (mean age 4.5 months at baseline), a cohort of 11 patients aged 6 months to less than 12 months (mean age 9.0 months at baseline), and a cohort of 19 patients aged 12 months to less than 24 months (mean age 15.2 months at baseline) in a 24-week, open-label clinical trial, administered 5.8 mg, 11.4 mg, 17.1 mg, 22.8 mg, 25 mg, 50 mg, or 75 mg (11.4 mg, 17.1 mg, and 22.8 mg are not recommended dosages) of ivacaftor granules twice daily (Trial 8). The safety profile of patients in this trial was similar to that observed in patients aged 2 years and older.
- Safety of KALYDECO in patients aged 1 month and older was evaluated in a 96-week, open-label study (Trial 9) in 86 patients (38 rolled over from Trial 8, and 48 KALYDECO-naïve). Adverse reactions from Trial 9 were generally similar to those reported in Trial 8.

The safety and effectiveness of KALYDECO in pediatric patients with CF younger than 1 month of age have not been established.

Juvenile Animal Toxicity Data

In a juvenile toxicology study in which ivacaftor was administered to rats from postnatal days 7 to 35, cataracts were observed at all dose levels, ranging from 0.1 to 0.8 times the MRHD (based on summed AUCs for ivacaftor and its metabolites at oral doses of 10-50 mg/kg/day). This finding has not been observed in older animals.

8.5 Geriatric Use

CF is largely a disease of children and young adults. Clinical trials of KALYDECO did not include sufficient numbers of patients 65 years of age and over to determine whether they respond differently from younger patients.

8.6 Hepatic Impairment

- Mild Hepatic Impairment (Child-Pugh Class A): No dosage adjustment is necessary for patients aged 6 months or older [see Clinical Pharmacology (12.3)].
- Moderate Hepatic Impairment (Child-Pugh Class B): A reduced dosage is recommended in patients aged 6 months or older [see Dosage and Administration (2.3) and Clinical Pharmacology (12.3)].
- Severe Hepatic Impairment (Child-Pugh Class C): Studies have not been conducted in patients with severe hepatic impairment (Child-Pugh Class C), but exposure is expected to be higher than in patients with moderate hepatic impairment. Therefore, use with caution at a reduced dosage, in patients aged 6 months or older with severe hepatic impairment after weighing the risks and benefits of treatment [see Dosage and Administration (2.3) and Clinical Pharmacology (12.3)].

Due to variability in maturation of cytochrome (CYP) enzymes involved in ivacaftor metabolism, treatment with KALYDECO is not recommended in patients aged 1 month to less than 6 months with any level of hepatic impairment [see Dosage and Administration (2.3)].

8.7 Renal Impairment

KALYDECO has not been studied in patients with mild, moderate, or severe renal impairment or in patients with end-stage renal disease. No dosage adjustment is necessary for patients with mild to moderate renal impairment; however, caution is recommended while using KALYDECO in patients with severe renal impairment (creatinine clearance less than or equal to 30 mL/min) or end-stage renal disease.

10 OVERDOSAGE

There have been no reports of overdose with KALYDECO.

No specific antidote is available for overdose with KALYDECO. Treatment of overdose with KALYDECO consists of general supportive measures including monitoring of vital signs and observation of the clinical status of the patient.

11 DESCRIPTION

The active ingredient in KALYDECO tablets and oral granules is ivacaftor, a cystic fibrosis transmembrane conductance regulator potentiator, which has the following chemical name: N-(2,4-di-tert-butyl-5-hydroxyphenyl)-1,4-dihydro-4-oxoquinoline-3-carboxamide. Its molecular formula is C24H28N2O3 and its molecular weight is 392.49. Ivacaftor has the following structural formula:

Ivacaftor is a white to off-white powder that is practically insoluble in water (<0.05 microgram/mL).

KALYDECO is available as a light blue, oblong-shaped, film-coated tablet for oral administration containing 150 mg of ivacaftor. Each KALYDECO tablet contains 150 mg of ivacaftor and the following inactive ingredients: colloidal silicon dioxide, croscarmellose sodium, hypromellose acetate succinate, lactose monohydrate, magnesium stearate, microcrystalline cellulose, and sodium lauryl sulfate. The tablet film coat contains carnauba wax, FD&C Blue #2, PEG 3350, polyvinyl alcohol, talc, and titanium dioxide. The printing ink contains ammonium hydroxide, iron oxide black, propylene glycol, and shellac.

KALYDECO is also available as white to off-white granules for oral administration (sweetened but unflavored) and enclosed in a unit-dose packet containing 5.8 mg of ivacaftor, 13.4 mg of ivacaftor, 25 mg of ivacaftor, 50 mg of ivacaftor, or 75 mg of ivacaftor. Each unit-dose packet of KALYDECO oral granules contains 5.8 mg of ivacaftor, 13.4 mg of ivacaftor, 25 mg of ivacaftor, 50 mg of ivacaftor, or 75 mg of ivacaftor and the following inactive ingredients: colloidal silicon dioxide, croscarmellose sodium, hypromellose acetate succinate, lactose monohydrate, magnesium stearate, mannitol, sucralose, and sodium lauryl sulfate.

12 CLINICAL PHARMACOLOGY

12.1 Mechanism of Action

Ivacaftor is a potentiator of the CFTR protein. The CFTR protein is a chloride channel present at the surface of epithelial cells in multiple organs. Ivacaftor facilitates increased chloride transport by potentiating the channel open probability (or gating) of CFTR protein located at the cell surface. The overall level of ivacaftor-mediated CFTR chloride transport is dependent on the amount of CFTR protein at the cell surface and how responsive a particular mutant CFTR protein is to ivacaftor potentiation.

CFTR Chloride Transport Assay in Fischer Rat Thyroid (FRT) cells expressing mutant CFTR

The chloride transport response of mutant CFTR protein to ivacaftor was determined in Ussing chamber electrophysiology studies using a panel of FRT cell lines transfected with individual CFTR mutations. Ivacaftor increased chloride transport in FRT cells expressing CFTR mutations that result in CFTR protein being delivered to the cell surface.

The in vitro CFTR chloride transport response threshold was designated as a net increase of at least 10% of normal over baseline because it is predictive or reasonably expected to predict clinical benefit. For individual mutations, the magnitude of the net change over baseline in CFTR-mediated chloride transport in vitro is not correlated with the magnitude of clinical response. A patient must have at least one CFTR mutation responsive to ivacaftor to be indicated.

Note that splice site mutations cannot be studied in the FRT assay. Evidence of clinical efficacy exists for non-canonical splice mutations 2789+5G→A, 3272-26A→G, 3849+10kbC→T, 711+3A→G and E831X and these are listed in Table 3 below [see also Clinical Studies (14.4)]. The G970R mutation causes a splicing defect resulting in little-to-no CFTR protein at the cell surface that can be potentiated by ivacaftor [see Clinical Studies (14.2)].

Ivacaftor also increased chloride transport in cultured human bronchial epithelial (HBE) cells derived from CF patients who carried F508del on one CFTR allele and either G551D or R117H-5T on the second CFTR allele.

Table 3 lists mutations that are responsive to ivacaftor based on 1) a positive clinical response and/or 2) in vitro data in FRT cells indicating that ivacaftor increases chloride transport to at least 10% over baseline (% of normal).

Table 3: List of CFTR Gene Mutations that Produce CFTR Protein and are Responsive to KALYDECO
711+3A→G [Clinical data exist for these mutations [see Clinical Studies (14)].] | F311del | I148T | R75Q | S589N
2789+5G→A | F311L | I175V | R117C | S737F
3272-26A→G | F508C | I807M | R117G | S945L
3849+10kbC→T | F508C;S1251N [Complex/compound mutations where a single allele of the CFTR gene has multiple mutations; these exist independent of the presence of mutations on the other allele.] | I1027T | R117H | S977F
A120T | F1052V | I1139V | R117L | S1159F
A234D | F1074L | K1060T | R117P | S1159P
A349V | G178E | L206W | R170H | S1251N
A455E | G178R | L320V | R347H | S1255P
A1067T | G194R | L967S | R347L | T338I
D110E | G314E | L997F | R352Q | T1053I
D110H | G551D | L1480P | R553Q | V232D
D192G | G551S | M152V | R668C | V562I
D579G | G576A | M952I | R792G | V754M
D924N | G970D | M952T | R933G | V1293G
D1152H | G1069R | P67L | R1070Q | W1282R
D1270N | G1244E | Q237E | R1070W | Y1014C
E56K | G1249R | Q237H | R1162L | Y1032C
E193K | G1349D | Q359R | R1283M
E822K | H939R | Q1291R | S549N
E831X | H1375P | R74W | S549R

12.2 Pharmacodynamics

Sweat Chloride Evaluation

Changes in sweat chloride (a biomarker) response to KALYDECO were evaluated in seven clinical trials [see Clinical Studies (14)]. In a two-part, randomized, double-blind, placebo-controlled, crossover clinical trial in patients with CF who had a G1244E, G1349D, G178R, G551S, G970R, S1251N, S1255P, S549N, or S549R mutation in the CFTR gene (Trial 4), the treatment difference in mean change in sweat chloride from baseline through 8 weeks of treatment was -49 mmol/L (95% CI -57, -41). The mean changes in sweat chloride for the mutations for which KALYDECO is indicated ranged from -51 to -8, whereas the range for individual subjects with the G970R mutation was -1 to -11 mmol/L. In an open-label clinical trial in 34 patients ages 2 to less than 6 years administered either 50 mg or 75 mg of ivacaftor twice daily (Trial 6), the mean absolute change from baseline in sweat chloride through 24 weeks of treatment was -45 mmol/L (95% CI -53, -38) [see Use in Specific Populations (8.4)]. In a randomized, double-blind, placebo-controlled, 2-period, 3-treatment, 8-week crossover study in patients with CF aged 12 years and older who were heterozygous for the F508del mutation and with a second CFTR mutation predicted to be responsive to ivacaftor (Trial 7), the treatment difference in mean change in sweat chloride from study baseline to the average of Week 4 and Week 8 of treatment for KALYDECO treated patients was -4.5 mmol/L (95% CI -6.7, -2.3). In a 24-week, open-label clinical trial in patients with CF aged less than 24 months administered 5.8 mg, 11.4 mg, 17.1 mg, 22.8 mg, 25 mg, 50 mg, or 75 mg (11.4 mg, 17.1 mg, and 22.8 mg are not recommended dosages) of ivacaftor twice daily (Trial 8), the mean absolute change from baseline in sweat chloride for patients aged 12 months to less than 24 months (n=10) was -73.5 mmol/L (95% CI -86.0, -61.0) at Week 24, the mean absolute change from baseline in sweat chloride for patients aged 6 months to less than 12 months (n=6) was -58.6 mmol/L (95% CI -75.9, -41.3) at Week 24, and the mean absolute change from baseline in sweat chloride for patients aged 4 months to less than 6 months (n=3) was -50 mmol/L (95% CI -93.1, -6.9) at Week 24. The mean absolute change from baseline in sweat chloride through 24 weeks for patients aged 1 month to less than 4 months (n=5) was -40.3 mmol/L (95% CI -76.6, -4.1) [see Use in Specific Populations (8.4)].

There was no direct correlation between decrease in sweat chloride levels and improvement in lung function (FEV1).

Cardiac Electrophysiology

The effect of multiple doses of ivacaftor 150 mg and 450 mg twice daily on QTc interval was evaluated in a randomized, placebo- and active-controlled (moxifloxacin 400 mg) four-period crossover thorough QT study in 72 healthy subjects. In a study with demonstrated ability to detect small effects, the upper bound of the one-sided 95% confidence interval for the largest placebo adjusted, baseline-corrected QTc based on Fridericia's correction method (QTcF) was below 10 ms, the threshold for regulatory concern.

12.3 Pharmacokinetics

The pharmacokinetics of ivacaftor is similar between healthy adult volunteers and patients with CF.

After oral administration of a single 150 mg dose to healthy volunteers in a fed state, peak plasma concentrations (Tmax) occurred at approximately 4 hours, and the mean (±SD) for AUC and Cmax were 10600 (5260) ng*hr/mL and 768 (233) ng/mL, respectively.

After every 12-hour dosing, steady-state plasma concentrations of ivacaftor were reached by days 3 to 5, with an accumulation ratio ranging from 2.2 to 2.9.

Absorption

The exposure of ivacaftor increased approximately 2.5- to 4-fold when given with food that contains fat. Therefore, KALYDECO should be administered with fat-containing food. Examples of fat-containing foods include eggs, butter, peanut butter, cheese pizza, whole-milk dairy products (such as whole milk, cheese, yogurt, breast milk, and infant formula), etc. The median (range) Tmax is approximately 4.0 (3.0; 6.0) hours in the fed state.

KALYDECO granules (2 × 75 mg) had similar bioavailability as the 150 mg tablet when given with fat-containing food in adult subjects. The effect of food on ivacaftor absorption is similar for KALYDECO granules and the 150 mg tablet formulation.

Distribution

Ivacaftor is approximately 99% bound to plasma proteins, primarily to alpha 1-acid glycoprotein and albumin. Ivacaftor does not bind to human red blood cells.

After oral administration of 150 mg every 12 hours for 7 days to healthy volunteers in a fed state, the mean (±SD) for apparent volume of distribution was 353 (122) L.

Elimination

The apparent terminal half-life was approximately 12 hours following a single dose. The mean apparent clearance (CL/F) of ivacaftor was similar for healthy subjects and patients with CF. The CL/F (SD) for the 150 mg dose was 17.3 (8.4) L/hr in healthy subjects.

Metabolism

Ivacaftor is extensively metabolized in humans. In vitro and clinical studies indicate that ivacaftor is primarily metabolized by CYP3A. M1 and M6 are the two major metabolites of ivacaftor in humans. M1 has approximately one-sixth the potency of ivacaftor and is considered pharmacologically active. M6 has less than one-fiftieth the potency of ivacaftor and is not considered pharmacologically active.

Excretion

Following oral administration, the majority of ivacaftor (87.8%) is eliminated in the feces after metabolic conversion. The major metabolites M1 and M6 accounted for approximately 65% of the total dose eliminated with 22% as M1 and 43% as M6. There was negligible urinary excretion of ivacaftor as unchanged parent.

Specific Populations

Pediatric Patients

The following conclusions about exposures between adults and the pediatric population are based on population PK analyses:

Table 4: Ivacaftor Exposure by Age Group, Mean (SD)
Age Group | Dose | AUCss (ng∙h/mL)
1 to less than 2 months (≥3 kg) [Patients 1 to less than 6 months of age were of ≥37 weeks gestational age.] | 5.8 mg q12h | 5490 (1310)
2 to less than 4 months (≥3 kg) | 13.4 mg q12h | 6730 (3650) [Exposures for 2 to less than 4 months of age are predictions based on simulations from the population PK model incorporating data for this age group.]
4 to less than 6 months (≥5 kg) | 25 mg q12h | 6480 (2520) [Values based on population PK modeling incorporating data from patients 4 to <6 months of age from Trial 8.]
6 to less than 12 months (5 kg to <7 kg) [Value based on data from a single patient; standard deviation not reported.] | 25 mg q12h | 5360
6 to less than 12 months (7 kg to <14 kg) | 50 mg q12h | 9390 (3120)
12 to less than 24 months (7 kg to <14 kg) | 50 mg q12h | 9050 (3050)
12 to less than 24 months (≥14 kg to <25 kg) | 75 mg q12h | 9600 (1800)
2 to less than 6 years (<14 kg) | 50 mg q12h | 10500 (4260)
2 to less than 6 years (≥14 kg to <25 kg) | 75 mg q12h | 11300 (3820)
6 to less than 12 years | 150 mg q12h | 20000 (8330)
12 to less than 18 years | 150 mg q12h | 9240 (3420)
Adults (≥18 years) | 150 mg q12h | 10700 (4100)

Patients with Hepatic Impairment

Adult subjects with moderately impaired hepatic function (Child-Pugh Class B) had similar ivacaftor Cmax, but an approximately twofold increase in ivacaftor AUC0-∞ compared with healthy subjects matched for demographics. Based on simulations of these results, a reduced KALYDECO dosage to one tablet or packet of granules once daily is recommended for patients with moderate hepatic impairment aged 6 months and older. The impact of mild hepatic impairment (Child-Pugh Class A) on the pharmacokinetics of ivacaftor has not been studied, but the increase in ivacaftor AUC0-∞ is expected to be less than twofold. Therefore, no dosage adjustment is necessary for patients with mild hepatic impairment aged 6 months and older. The impact of severe hepatic impairment (Child-Pugh Class C) on the pharmacokinetics of ivacaftor has not been studied. The magnitude of increase in exposure in these patients is unknown but is expected to be substantially higher than that observed in patients with moderate hepatic impairment. When benefits are expected to outweigh the risks, KALYDECO should be used with caution in patients with severe hepatic impairment aged 6 months and older at a dosage of one tablet or one packet of granules given once daily or less frequently [see Dosage and Administration (2.3) and Use in Specific Populations (8.6)]. KALYDECO is not recommended in patients aged 1 month to less than 6 months with any level of hepatic impairment.

Patients with Renal Impairment

KALYDECO has not been studied in patients with mild, moderate, or severe renal impairment (creatinine clearance less than or equal to 30 mL/min) or in patients with end-stage renal disease. No dosage adjustments are recommended for mild and moderate renal impairment patients because of minimal elimination of ivacaftor and its metabolites in urine (only 6.6% of total radioactivity was recovered in the urine in a human PK study); however, caution is recommended when administering KALYDECO to patients with severe renal impairment or end-stage renal disease.

Male and Female Patients

The effect of gender on KALYDECO pharmacokinetics was evaluated using population pharmacokinetics of data from clinical studies of KALYDECO. No dosage adjustments are necessary based on gender.

Drug Interaction Studies

Drug interaction studies were performed with KALYDECO and other drugs likely to be co-administered or drugs commonly used as probes for pharmacokinetic interaction studies [see Drug Interactions (7)].

Dosing recommendations based on clinical studies or potential drug interactions with KALYDECO are presented below.

Potential for Ivacaftor to Affect Other Drugs

Based on in vitro results, ivacaftor and metabolite M1 have the potential to inhibit CYP3A and P-gp. Clinical studies showed that KALYDECO is a weak inhibitor of CYP3A and P-gp, but not an inhibitor of CYP2C8. In vitro studies suggest that ivacaftor and M1 may inhibit CYP2C9. In vitro, ivacaftor, M1, and M6 were not inducers of CYP isozymes. Dosing recommendations for co-administered drugs with KALYDECO are shown in Figure 1.

Figure 1: Impact of KALYDECO on Other Drugs

Note: The data obtained with substrates but without co-administration of KALYDECO are used as reference.
* NE: Norethindrone; ** EE: Ethinyl Estradiol
The vertical lines are at 0.8, 1.0, and 1.25, respectively.

Potential for Other Drugs to Affect Ivacaftor

In vitro studies showed that ivacaftor and metabolite M1 were substrates of CYP3A enzymes (i.e., CYP3A4 and CYP3A5). Exposure to ivacaftor is reduced by concomitant CYP3A inducers and increased by concomitant CYP3A inhibitors [see Dosage and Administration (2.4) and Drug Interactions (7)]. KALYDECO dosing recommendations for co-administration with other drugs are shown in Figure 2.

Figure 2: Impact of Other Drugs on KALYDECO

Note: The data obtained for KALYDECO without co-administration of inducers or inhibitors are used as reference.
The vertical lines are at 0.8, 1.0, and 1.25, respectively.

13 NONCLINICAL TOXICOLOGY

13.1 Carcinogenesis, Mutagenesis, Impairment of Fertility

Two-year studies were conducted in CD-1 mice and Sprague-Dawley rats to assess carcinogenic potential of KALYDECO. No evidence of tumorigenicity was observed in mice or rats at ivacaftor oral doses up to 200 mg/kg/day and 50 mg/kg/day, respectively (approximately equal to 1 and 4 times the MRHD based on summed AUCs of ivacaftor and its metabolites).

Ivacaftor was negative for genotoxicity in the following assays: Ames test for bacterial gene mutation, in vitro chromosomal aberration assay in Chinese hamster ovary cells, and in vivo mouse micronucleus test.

Ivacaftor impaired fertility and reproductive performance indices in male and female rats at 200 mg/kg/day (yielding exposures approximately 8 and 5 times, respectively, the MRHD based on summed AUCs of ivacaftor and its major metabolites). Increases in prolonged diestrus were observed in females at 200 mg/kg/day. Ivacaftor also increased the number of females with all nonviable embryos and decreased corpora lutea, implantations, and viable embryos in rats at 200 mg/kg/day (approximately 5 times the MRHD based on summed AUCs of ivacaftor and its major metabolites) when dams were dosed prior to and during early pregnancy. These impairments of fertility and reproductive performance in male and female rats at 200 mg/kg/day were attributed to severe toxicity. No effects on male or female fertility and reproductive performance indices were observed at ≤100 mg/kg/day (yielding exposures approximately 6 and 3 times, respectively, the MRHD based on summed AUCs of ivacaftor and its major metabolites).

14 CLINICAL STUDIES

14.1 Trials in Patients with CF who have a G551D Mutation in the CFTR Gene

Dose Ranging:

Dose ranging for the clinical program consisted primarily of one double-blind, placebo-controlled, crossover trial in 39 adult (mean age 31 years) Caucasian patients with CF who had FEV1 ≥40% predicted. Twenty patients with median predicted FEV1 at baseline of 56% (range: 42% to 109%) received KALYDECO 25, 75, 150 mg, or placebo every 12 hours for 14 days and 19 patients with median predicted FEV1 at baseline of 69% (range: 40% to 122%) received KALYDECO 150, 250 mg, or placebo every 12 hours for 28 days. The selection of the 150 mg every 12 hours dose was primarily based on nominal improvements in lung function (pre-dose FEV1) and changes in pharmacodynamic parameters (sweat chloride and nasal potential difference). The twice-daily dosing regimen was primarily based on an apparent terminal plasma half-life of approximately 12 hours.

Efficacy:

The efficacy of KALYDECO in patients with CF who have a G551D mutation in the CFTR gene was evaluated in two randomized, double-blind, placebo-controlled clinical trials in 213 clinically stable patients with CF (109 receiving KALYDECO 150 mg twice daily). All eligible patients from these trials were rolled over into an open-label extension study.

Trial 1 evaluated 161 patients with CF who were 12 years of age or older (mean age 26 years) with FEV1 at screening between 40-90% predicted [mean FEV1 64% predicted at baseline (range: 32% to 98%)]. Trial 2 evaluated 52 patients who were 6 to 11 years of age (mean age 9 years) with FEV1 at screening between 40-105% predicted [mean FEV1 84% predicted at baseline (range: 44% to 134%)]. Patients who had persistent Burkholderia cenocepacia, Burkholderia dolosa, or Mycobacterium abscessus isolated from sputum at screening and those with abnormal liver function defined as 3 or more liver function tests (ALT, AST, AP, GGT, total bilirubin) ≥3 times the ULN were excluded.

Patients in both trials were randomized 1:1 to receive either 150 mg of KALYDECO or placebo every 12 hours with fat-containing food for 48 weeks in addition to their prescribed CF therapies (e.g., tobramycin, dornase alfa). The use of inhaled hypertonic saline was not permitted.

The primary efficacy endpoint in both studies was improvement in lung function as determined by the mean absolute change from baseline in percent predicted pre-dose FEV1 through 24 weeks of treatment.

In both studies, treatment with KALYDECO resulted in a significant improvement in FEV1. The treatment difference between KALYDECO and placebo for the mean absolute change in percent predicted FEV1 from baseline through Week 24 was 10.6 percentage points (P<0.0001) in Trial 1 and 12.5 percentage points (P<0.0001) in Trial 2 (Figure 3). These changes persisted through 48 weeks. Improvements in percent predicted FEV1 were observed regardless of age, disease severity, sex, and geographic region.

Figure 3: Mean Absolute Change from Baseline in Percent Predicted FEV1 [Primary endpoint was assessed at the 24-week time point.]

Other efficacy variables included absolute change from baseline in sweat chloride [see Clinical Pharmacology (12.2)], time to first pulmonary exacerbation (Trial 1 only), absolute change from baseline in weight, and improvement from baseline in Cystic Fibrosis Questionnaire Revised (CFQ-R) respiratory domain score, a measure of respiratory symptoms relevant to patients with CF such as cough, sputum production, and difficulty breathing. For the purpose of the study, a pulmonary exacerbation was defined as a change in antibiotic therapy (IV, inhaled, or oral) as a result of 4 or more of 12 pre-specified sino-pulmonary signs/symptoms. Patients treated with KALYDECO demonstrated statistically significant improvements in risk of pulmonary exacerbations, CF symptoms (in Trial 1 only), and gain in body weight (Table 5). Weight data, when expressed as body mass index normalized for age and sex in patients <20 years of age, were consistent with absolute change from baseline in weight.

Table 5: Effect of KALYDECO on Other Efficacy Endpoints in Trials 1 and 2
 | Trial 1 |  | Trial 2
Endpoint | Treatment difference [Treatment difference = effect of KALYDECO – effect of Placebo.] (95% CI) | P value | Treatment difference (95% CI) | P value
Mean absolute change from baseline in CFQ-R respiratory domain score (points)
Through Week 24 | 8.1 (4.7, 11.4) | <0.0001 | 6.1 (-1.4, 13.5) | 0.1092
Through Week 48 | 8.6 (5.3, 11.9) | <0.0001 | 5.1 (-1.6, 11.8) | 0.1354
Relative risk of pulmonary exacerbation
Through Week 24 | 0.40 [Hazard ratio for time to first pulmonary exacerbation.] | 0.0016 | NA | NA
Through Week 48 | 0.46 | 0.0012 | NA | NA
Mean absolute change from baseline in body weight (kg)
At Week 24 | 2.8 (1.8, 3.7) | <0.0001 | 1.9 (0.9, 2.9) | 0.0004
At Week 48 | 2.7 (1.3, 4.1) | 0.0001 | 2.8 (1.3, 4.2) | 0.0002
Absolute change in sweat chloride (mmol/L)
Through Week 24 | -48 (-51, -45) | <0.0001 | -54 (-62, -47) | <0.0001
Through Week 48 | -48 (-51, -45) | <0.0001 | -53 (-61, -46) | <0.0001
CI: confidence interval; NA: not analyzed due to low incidence of events.

14.2 Trial in Patients with a G1244E, G1349D, G178R, G551S, G970R, S1251N, S1255P, S549N, or S549R Mutation in the CFTR Gene

The efficacy and safety of KALYDECO in patients with CF who have a G1244E, G1349D, G178R, G551S, G970R, S1251N, S1255P, S549N, or S549R mutation in the CFTR gene were evaluated in a two-part, randomized, double-blind, placebo-controlled, crossover design clinical trial in 39 patients with CF (Trial 4). Patients who completed Part 1 of this trial continued into the 16-week open-label Part 2 of the study. The mutations studied were G178R, S549N, S549R, G551S, G970R, G1244E, S1251N, S1255P, and G1349D. See Clinical Studies (14.1) for efficacy in patients with a G551D mutation.

Patients were 6 years of age or older (mean age 23 years) with FEV1 ≥40% at screening [mean FEV1 at baseline 78% predicted (range: 43% to 119%)]. Patients with evidence of colonization with Burkholderia cenocepacia, Burkholderia dolosa, or Mycobacterium abscessus and those with abnormal liver function defined as 3 or more liver function tests (ALT, AST, AP, GGT, total bilirubin) ≥3 times the ULN at screening were excluded.

Patients were randomized 1:1 to receive either 150 mg of KALYDECO or placebo every 12 hours with fat-containing food for 8 weeks in addition to their prescribed CF therapies during the first treatment period and crossed over to the other treatment for the second 8 weeks. The two 8-week treatment periods were separated by a 4- to 8-week washout period. The use of inhaled hypertonic saline was not permitted.

The primary efficacy endpoint was improvement in lung function as determined by the mean absolute change from baseline in percent predicted FEV1 through 8 weeks of treatment. Other efficacy variables included absolute change from baseline in sweat chloride through 8 weeks of treatment [see Clinical Pharmacology (12.2)], absolute change from baseline in body mass index (BMI) at 8 weeks of treatment (including body weight at 8 weeks), and improvement in CFQ-R respiratory domain score through 8 weeks of treatment. For the overall population of the 9 mutations studied, treatment with KALYDECO compared to placebo resulted in significant improvement in percent predicted FEV1 [10.7 through Week 8 (P<0.0001)], BMI [0.66 kg/m^2 at Week 8 (P<0.0001)], and CFQ-R respiratory domain score [9.6 through Week 8 (P=0.0004)]; however, there was a high degree of variability of efficacy responses among the 9 mutations (Table 6).

Table 6: Effect of KALYDECO for Efficacy Variables in the Overall Populations and for Specific CFTR Mutations
Mutation (n) | Absolute change in percent predicted FEV1 |  |  | BMI (kg/m^2) | CFQ-R Respiratory Domain Score (Points) | Absolute Change in Sweat Chloride (mmol/L)
 | At Week 2 | At Week 4 | At Week 8 | At Week 8 | At Week 8 | At Week 8
All patients (n=39)
Results shown as mean (95% CI) change from baseline KALYDECO vs. placebo-treated patients:
 | 8.3 (4.5, 12.1) | 10.0 (6.2, 13.8) | 13.8 (9.9, 17.6) | 0.66 [Result for weight gain as a component of body mass index was consistent with BMI.] (0.34, 0.99) | 12.8 (6.7, 18.9) | -50 (-58, -41) [n=36 for the analysis of absolute change in sweat chloride.]
Patients grouped under mutation types (n)
Results shown as mean (minimum, maximum) for change from baseline for KALYDECO-treated patients: [Statistical testing was not performed due to small numbers for individual mutations.]
G1244E (5) | 11 (-5, 25) | 6 (-5, 13) | 8 (-1, 18) | 0.63 (0.34, 1.32) | 3.3 (-27.8, 22.2) | -55 (-75, -34)
G1349D (2) | 19 (5, 33) | 18 (2, 35) | 20 (3, 36) | 1.15 (1.07, 1.22) | 16.7 (-11.1, 44.4) | -80 (-82, -79)
G178R (5) | 7 (1, 17) | 10 (-2, 21) | 8 (-1, 18) | 0.85 (0.33, 1.46) | 20.0 (5.6, 50.0) | -53 (-65, -35)
G551S (2) | 0 (-5, 5) | 0.3 (-5, 6) | 3 [Reflects results from the one patient with the G551S mutation with data at the 8-week time point.] | 0.16 | 16.7 | -68
G970R (4) | 7 (1, 13) | 7 (1, 14) | 3 (-1, 5) | 0.48 (-0.38, 1.75) | 1.4 (-16.7, 16.7) | -6 (-16, -2)
S1251N (8) | 2 (-23, 20) | 8 (-13, 26) | 9 (-20, 21) | 0.73 (0.08, 1.83) | 23.3 (5.6, 50.0) | -54 (-84, -7)
S1255P (2) | 11 (8, 14) | 9 (5, 13) | 3 (-1, 8) | 1.62 (1.39, 1.84) | 8.3 (5.6, 11.1) | -78 (-82, -74)
S549N (6) | 11 (5, 16) | 8 (-9, 19) | 11 (-2, 20) | 0.79 (0.00, 1.91) | 8.8 (-8.3, 27.8) | -74 (-93, -53)
S549R (4) | 3 (-4, 8) | 4 (-4, 10) | 5 (-3, 13) | 0.53 (0.33, 0.80) | 6.9 (0.0, 11.1) | -61 [n=3 for the analysis of absolute change in sweat chloride.] (-71, -54)

14.3 Trial in Patients with CF who have an R117H Mutation in the CFTR Gene

The efficacy and safety of KALYDECO in patients with CF who have an R117H mutation in the CFTR gene were evaluated in a randomized, double-blind, placebo-controlled, parallel-group clinical trial (Trial 5). Fifty-nine of 69 patients completed 24 weeks of treatment. Two patients discontinued and 8 patients did not complete treatment due to study termination. Trial 5 evaluated 69 clinically stable patients with CF who were 6 years of age or older (mean age 31 years). Patients who were aged 12 years and older had FEV1 at screening between 40-90% predicted, and patients who were 6-11 years of age had FEV1 at screening between 40-105% predicted. The overall mean FEV1 was 73% predicted at baseline (range: 33% to 106%). The patients had well preserved BMIs (mean overall: 23.76 kg/m^2) and a high proportion were pancreatic sufficient as assessed by a low rate of pancreatic enzyme replacement therapy use (pancreatin: 11.6%; pancrelipase: 5.8%). Patients who had persistent Burkholderia cenocepacia, Burkholderia dolosa, or Mycobacterium abscessus isolated from sputum at screening, and those with abnormal liver function defined as 3 or more liver function tests (ALT, AST, AP, GGT, total bilirubin) ≥3 times the ULN, were excluded.

Patients were randomized 1:1 to receive either 150 mg of KALYDECO (n=34) or placebo (n=35) every 12 hours with fat-containing food for 24 weeks in addition to their prescribed CF therapies.

The primary efficacy endpoint was improvement in lung function as determined by the mean absolute change from baseline in percent predicted FEV1 through 24 weeks of treatment. The treatment difference for absolute change in percent predicted FEV1 through Week 24 was 2.1 percentage points (analysis conducted with the full analysis set which included all 69 patients) and did not reach statistical significance (Table 7).

Other efficacy variables that were analyzed included absolute change in sweat chloride from baseline through Week 24, improvement in cystic fibrosis respiratory symptoms through Week 24 as assessed by the CFQ-R respiratory domain score (Table 7), absolute change in body mass index (BMI) at Week 24, and time to first pulmonary exacerbation. The overall treatment difference for the absolute change from baseline in BMI at Week 24 was 0.3 kg/m^2 and the calculated hazard ratio for time to first pulmonary exacerbation was 0.93, which were not statistically significant.

Statistically significant improvements in clinical efficacy (FEV1, CFQ-R respiratory domain score) were seen in several subgroup analyses and decreases in sweat chloride were observed in all subgroups. The mean baseline sweat chloride for all patients was 70 mmol/L. Subgroups analyzed included those based on age, lung function, and poly-T status (Table 7).

Table 7: Effect of KALYDECO on Overall Population (Percent Predicted FEV1, CFQ-R Respiratory Domain Score, and Sweat Chloride) and in Relevant Subgroups Through 24 Weeks
 |  | Absolute Change through Week 24 [MMRM analysis with fixed effects for treatment, age, week, baseline value, treatment by week, and subject as a random effect.] - All Randomized Patients
 |  | % Predicted FEV1 (Percentage Points) |  |  | CFQ-R Respiratory Domain Score (Points) |  |  | Sweat Chloride (mmol/L)
Subgroup Parameter | Study Drug | n | Mean | Treatment Difference (95% CI) | n | Mean | Treatment Difference (95% CI) | n | Mean | Treatment Difference (95% CI)
R117H–All Patients
 | Placebo KALYDECO | 35 34 | 0.5 2.6 | 2.1 (-1.1, 5.4) | 34 33 | -0.8 7.6 | 8.4 (2.2, 14.6) | 35 32 | -2.3 -26.3 | -24.0 (-28.0, -19.9)
Subgroup by Age
6-11 | Placebo KALYDECO | 8 9 | 3.5 -2.8 | -6.3 (-12.0, -0.7) | 7 8 | -1.6 -7.7 | -6.1 (-15.7, 3.4) | 8 8 | 1.0 -26.6 | -27.6 (-37.2, -18.1)
12-17 | Placebo KALYDECO | 1 1 | --- | --- | 1 1 | --- | --- | 1 1 | --- | ---
≥18 | Placebo KALYDECO | 26 24 | -0.5 4.5 | 5.0 (1.1, 8.8) | 26 24 | -0.5 12.2 | 12.6 (5.0, 20.3) | 26 23 | -4.0 -25.9 | -21.9 (-26.5, -17.3)
Subgroup by Poly-T Status [(n=54) Poly-T status confirmed by genotyping.]
5T | Placebo KALYDECO | 24 14 | 0.7 6.0 | 5.3 (1.3, 9.3) | 24 14 | -0.6 14.7 | 15.3 (7.7, 23.0) | 24 13 | -4.6 -28.7 | -24.2 (-30.2, -18.2)
7T | Placebo KALYDECO | 5 11 | -0.9 -0.7 | 0.2 (-8.1, 8.5) | 5 11 | -6.0 -0.7 | 5.2 (-13.0, 23.4) | 5 10 | 3.9 -20.2 | -24.1 (-33.9, -14.3)
Subgroup by Baseline FEV1 % Predicted
<70% | Placebo KALYDECO | 15 13 | 0.4 4.5 | 4.0 (-2.1, 10.1) | 15 13 | 3.0 14.4 | 11.4 (1.2, 21.6) | 15 12 | -3.8 -29.3 | -25.5 (-31.8, -19.3)
70-90% | Placebo KALYDECO | 14 14 | 0.2 2.8 | 2.6 (-2.3, 7.5) | 13 14 | -3.6 5.2 | 8.8 (-2.6, 20.2) | 14 14 | -3.1 -23.0 | -20.0 (-26.9, -12.9)
>90% | Placebo KALYDECO | 6 7 | 2.2 -2.1 | -4.3 (-9.9, 1.3) | 6 6 | -2.5 -3.2 | -0.7 (-10.4, 9.0) | 6 6 | 1.0 -25.9 | -26.8 (-39.5, -14.1)

14.4 Trial in Patients with CF Heterozygous for the F508del Mutation and a Second Mutation Predicted to be Responsive to Ivacaftor

The efficacy and safety of KALYDECO and an ivacaftor-containing combination product in 246 patients with CF was evaluated in a randomized, double-blind, placebo-controlled, 2-period, 3-treatment, 8-week crossover design clinical trial (Trial 7). Mutations predicted to be responsive to ivacaftor were selected for the study based on the clinical phenotype (pancreatic sufficiency), biomarker data (sweat chloride), and in vitro responsiveness to ivacaftor.

Eligible patients were heterozygous for the F508del mutation with a second mutation predicted to be responsive to ivacaftor. Of the 244 patients included in the efficacy analysis, who were randomized and dosed, 146 patients had a splice mutation and 98 patients had a missense mutation, as the second allele. 156 patients received KALYDECO and 161 patients received placebo. Patients were aged 12 years and older (mean age 35 years [range 12-72]) and had a percent predicted FEV1 at screening between 40-90 [mean ppFEV1 at study baseline 62 (range: 35 to 94)]. Patients with evidence of colonization with organisms associated with a more rapid decline in pulmonary status (e.g., Burkholderia cenocepacia, Burkholderia dolosa, or Mycobacterium abscessus) and those with abnormal liver function at screening were excluded. Abnormal liver function was defined as 2 or more liver function tests (ALT, AST, ALP, GGT) ≥3 times the ULN or total bilirubin ≥2 times the ULN, or a single increase in ALT/AST ≥5 times the ULN.

The primary efficacy endpoint was the mean absolute change from study baseline in percent predicted FEV1 averaged at Weeks 4 and 8 of treatment. The key secondary efficacy endpoint was absolute change in CFQ-R respiratory domain score from study baseline averaged at Weeks 4 and 8 of treatment. For the overall population, treatment with KALYDECO compared to placebo resulted in significant improvement in ppFEV1 [4.7 percent points from study baseline to average of Week 4 and Week 8 (P<0.0001)] and CFQ-R respiratory domain score [9.7 points from study baseline to average of Week 4 and Week 8 (P<0.0001)]. Statistically significant improvements compared to placebo were also observed in the subgroup of patients with splice mutations and missense mutations (Table 8).

Table 8: Effect of KALYDECO for Efficacy Variables
Mutation (n) | Absolute Change in percent predicted FEV1 [Average of Week 4 and 8 values.] [Absolute change in ppFEV1 by individual mutations is an ad hoc analysis.] | Absolute Change in CFQ-R Respiratory Domain Score (Points) [Absolute change in CFQ-R respiratory domain score and absolute change in sweat chloride by mutation subgroups and by individual mutations are ad hoc analyses.] | Absolute Change in Sweat Chloride (mmol/L)
Splice mutations (n=94 for IVA and n=97 for PBO)
Results shown as difference in mean (95% CI) change from study baseline for KALYDECO vs. placebo-treated patients:
 | 5.4 (4.1, 6.8) | 8.5 (5.3, 11.7) | -2.4 (-5.0, 0.3)
By individual splice mutation (n). Results shown as mean (minimum, maximum) for change from study baseline for KALYDECO-treated patients
2789+5G→A (28) | 5.1 (-7.1, 17.0) | 8.6 (-5.6, 27.8) | 0.4 (-7.5, 8.8)
3272-26A→G (23) | 3.5 (-9.1, 16.0) | 8.0 (-11.1, 27.8) | -2.3 (-25.0, 11.8)
3849+10kbC→T (40) | 5.1 (-6.8, 16.2) | 7.5 (-30.6, 55.6) | -4.6 (-80.5, 23.0)
711+3A→G (2) | 9.2 (8.9, 9.6) | -8.3 (-13.9, -2.8) | -9.9 (-13.5, -6.3)
E831X (1) | 7.1 (7.1, 7.1) | 0.0 (0.0, 0.0) | -7.8 (-7.8, -7.8)
Missense mutations (n=62 for IVA and n=63 for PBO)
Results shown as difference in mean (95% CI) change from study baseline for KALYDECO vs. placebo-treated patients:
 | 3.6 (1.9, 5.2) | 11.5 (7.5, 15.4) | -7.8 (-11.2, -4.5)
By individual missense mutation (n). Results shown as mean (minimum, maximum) for change from study baseline for KALYDECO-treated patients
D579G (2) | 13.3 (12.4, 14.1) | 15.3 (-2.8, 33.3) | -30.8 (-36.0, -25.5)
D1152H (15) | 2.4 (-5.0, 10.2) | 13.7 (-16.7, 50.0) | -4.8 (-22.0, 3.0)
A455E (14) | 3.7 (-6.6, 19.7) | 6.8 (-13.9, 33.3) | 7.5 (-16.8, 16.0)
L206W (2) | 4.2 (2.5, 5.9) | 12.5 (-5.6, 30.6) | 3.9 (-8.3, 16.0)
P67L (12) | 4.3 (-2.5, 25.7) | 10.8 (-12.5, 36.1) | -10.5 (-34.8, 9.8)
R1070W (1) | 2.9 (2.9, 2.9) | 44.4 (44.4, 44.4) | 0.3 (0.3, 0.3)
R117C (1) | 3.5 (3.5, 3.5) | 22.2 (22.2, 22.2) | -36.0 (-36.0, -36.0)
R347H (3) | 2.5 (-0.6, 6.9) | 6.5 (5.6, 8.3) | -19.2 (-25.8, -7.0)
R352Q (2) | 4.4 (3.5, 5.3) | 9.7 (8.3, 11.1) | -21.9 (-45.5, 1.8)
S945L (9) | 8.8 (-0.2, 20.5) | 10.6 (-25.0, 27.8) | -30.8 (-50.8, -17.3)
S977F (1) | 4.3 (4.3, 4.3) | -2.8 (-2.8, -2.8) | -19.5 (-19.5, -19.5)

In an analysis of BMI at Week 8, an exploratory endpoint, patients treated with KALYDECO had a mean improvement of 0.28 kg/m^2 [95% CI (0.14, 0.43)], 0.24 kg/m^2 [95% CI (0.06, 0.43)], and 0.35 kg/m^2 [95% CI (0.12, 0.58)] versus placebo for the overall, splice, and missense mutation populations of patients, respectively.

14.5 Trial in Patients Homozygous for the F508del Mutation in the CFTR Gene

Trial 3 was a 16-week, randomized, double-blind, placebo-controlled, parallel-group trial in 140 patients with CF aged 12 years and older who were homozygous for the F508del mutation in the CFTR gene and who had FEV1 ≥40% predicted. Patients were randomized 4:1 to receive KALYDECO 150 mg (n=112) every 12 hours or placebo (n=28) in addition to their prescribed CF therapies. The mean age of patients enrolled was 23 years and the mean baseline FEV1 was 79% predicted (range: 40% to 129%). As in Trials 1 and 2, patients who had persistent Burkholderia cenocepacia, Burkholderia dolosa, or Mycobacterium abscessus isolated from sputum at screening and those with abnormal liver function defined as 3 or more liver function tests (ALT, AST, AP, GGT, total bilirubin) ≥3 times the ULN were excluded. The use of inhaled hypertonic saline was not permitted.

The primary endpoint was improvement in lung function as determined by the mean absolute change from baseline through Week 16 in percent predicted FEV1. The treatment difference from placebo for the mean absolute change in percent predicted FEV1 through Week 16 in patients with CF homozygous for the F508del mutation in the CFTR gene was 1.72 percentage points (1.5% and -0.2% for patients in the KALYDECO and placebo-treated groups, respectively) and did not reach statistical significance (Table 9).

Other efficacy variables that were analyzed included absolute change in sweat chloride from baseline through Week 16, change in cystic fibrosis respiratory symptoms through Week 16 as assessed by the CFQ-R respiratory domain score (Table 9), change in weight through Week 16, and rate of pulmonary exacerbation. The overall treatment difference for change from baseline in weight through Week 16 was -0.16 kg (95% CI -1.06, 0.74); the rate ratio for pulmonary exacerbation was 0.677 (95% CI 0.33, 1.37).

Table 9: Effect of KALYDECO on Overall Population (Percent Predicted FEV1, CFQ-R Respiratory Domain Score, and Sweat Chloride) Through 16 Weeks
 |  | Absolute Change through Week 16 [MMRM analysis with fixed effects for treatment, age week, baseline value, treatment by week, and subject as a random effect.] - Full Analysis Set
 |  | % Predicted FEV1 (Percentage Points) |  |  | CFQ-R Respiratory Domain Score (Points) |  |  | Sweat Chloride (mmol/L)
Subgroup Parameter | Study Drug | n | Mean | Treatment Difference (95% CI) | n | Mean | Treatment Difference (95% CI) | n | Mean | Treatment Difference (95% CI)
F508del homozygous
 | Placebo KALYDECO | 28 111 | -0.2 1.5 | 1.72 (-0.6, 4.1) | 28 111 | -1.44 -0.12 | 1.3 (-2.9, 5.6) | 28 109 | 0.13 -2.74 | -2.9 (-5.6, -0.2)

16 HOW SUPPLIED/STORAGE AND HANDLING

KALYDECO (ivacaftor) tablets are supplied as light blue, film-coated, oblong-shaped tablets containing 150 mg of ivacaftor. Each tablet is printed with the characters "V 150" on one side and plain on the other, and is packaged as follows:

 | 56-count carton (contains 4 individual blister cards of 14 tablets per card) | NDC 51167-200-01
 | 60-count bottle | NDC 51167-200-02

KALYDECO (ivacaftor) oral granules are supplied as small, white to off-white granules and enclosed in unit-dose packets as follows:

 | 56-count carton (contains 56 unit-dose packets of 5.8 mg ivacaftor per packet) | NDC 51167-785-01
 | 56-count carton (contains 56 unit-dose packets of 13.4 mg ivacaftor per packet) | NDC 51167-770-01
 | 56-count carton (contains 56 unit-dose packets of 25 mg ivacaftor per packet) | NDC 51167-600-01
 | 56-count carton (contains 56 unit-dose packets of 50 mg ivacaftor per packet) | NDC 51167-300-01
 | 56-count carton (contains 56 unit-dose packets of 75 mg ivacaftor per packet) | NDC 51167-400-01

STORAGE AND HANDLING

Store at 20°C-25°C (68°F-77°F); excursions permitted to 15°C-30°C (59°F-86°F) [see USP Controlled Room Temperature].

17 PATIENT COUNSELING INFORMATION

Advise the patient to read the FDA-approved patient labeling (Patient Information).

Transaminase (ALT or AST) Elevations and Monitoring

Inform patients that elevation in liver tests have occurred in patients treated with KALYDECO. Liver function tests will be performed prior to initiating KALYDECO, every 3 months during the first year of treatment and annually thereafter. More frequent monitoring of liver function tests should be considered in patients with a history of transaminase elevations [see Warnings and Precautions (5.1)].

Hypersensitivity Reactions, Including Anaphylaxis

Hypersensitivity reactions including anaphylaxis are possible with use of KALYDECO. Inform patients of the early signs of hypersensitivity reactions including rash, hives, itching, facial swelling, tightness of the chest and wheezing. Advise patients to discontinue use of KALYDECO immediately and contact their physician or go to the emergency department if these symptoms occur.

Intracranial Hypertension

Inform patients that intracranial hypertension has occurred in patients who received drugs containing the same or similar active ingredients as KALYDECO. Instruct patients to notify their healthcare provider right away if they experience signs and symptoms of intracranial hypertension, including headache, blurred vision, diplopia, and vision loss [see Warnings and Precautions (5.3)].

Drug Interactions with CYP3A Inducers and Inhibitors

Ask patients to tell you all the medications they are taking including any herbal supplements or vitamins. Co-administration of KALYDECO with strong CYP3A inducers (e.g., rifampin, St. John's wort) is not recommended, as they may reduce the therapeutic effectiveness of KALYDECO. Dosage reduction is recommended when patients aged 6 months and older are taking concomitant strong CYP3A inhibitors, such as ketoconazole, or moderate CYP3A inhibitors, such as fluconazole [see Dosage and Administration (2.4) and Drug Interactions (7.1)]. Treatment with KALYDECO is not recommended in patients aged 1 month to less than 6 months who are taking concomitant moderate or strong CYP3A inhibitors. Food or drink containing grapefruit should be avoided [see Drug Interactions (7.1, 7.2) and Clinical Pharmacology (12.3)].

Use in Patients with Hepatic Impairment

Inquire and/or assess whether patients have liver impairment. Reduce the dosage of KALYDECO in patients aged 6 months and older with moderately impaired hepatic function (Child-Pugh Class B) to one tablet or one packet of granules once daily. KALYDECO has not been studied in patients with severe hepatic impairment (Child-Pugh Class C); however, exposure is expected to be substantially higher than that observed in patients with moderate hepatic impairment. When benefits are expected to outweigh the risks, KALYDECO should be used with caution in patients aged 6 months and older with severe hepatic impairment at a reduced dosage [see Dosage and Administration (2.3)]. Treatment with KALYDECO is not recommended in patients aged 1 month to less than 6 months with any signs of hepatic impairment. No dosage adjustment is recommended for patients 6 months and older with mild hepatic impairment (Child-Pugh Class A) [see Use in Specific Populations (8.6)].

Driving and Operating Machinery

Dizziness has been reported in patients receiving KALYDECO, which could influence the ability to drive or operate machines [see Adverse Reactions (6.1)]. Advise patients not to drive or operate machines if they experience dizziness until symptoms abate.

Administration

KALYDECO (ivacaftor) tablets 150 mg

Inform patients that KALYDECO tablet is best absorbed by the body when taken with food that contains fat. A typical CF diet will satisfy this requirement. Examples include eggs, butter, peanut butter, cheese pizza, whole-milk dairy products (such as whole milk, cheese, and yogurt), etc.

KALYDECO (ivacaftor) oral granules 5.8 mg, 13.4 mg, 25 mg, 50 mg, or 75 mg

Inform patients and caregivers that KALYDECO oral granules should be mixed with one teaspoon (5 mL) of age-appropriate soft food or liquid and completely consumed to ensure delivery of the entire dose. Food or liquid should be at or below room temperature. Once mixed, the product has been shown to be stable for one hour, and therefore should be consumed during this period. Some examples of appropriate soft foods or liquids may include puréed fruits or vegetables, yogurt, applesauce, water, breast milk, infant formula, milk, or juice.

Inform patients and caregivers that KALYDECO is best absorbed by the body when taken with food that contains fat; therefore, KALYDECO oral granules should be taken just before or just after consuming food that contains fat. A typical CF diet will satisfy this requirement. Examples include eggs, butter, peanut butter, cheese pizza, whole-milk dairy products (such as whole milk, cheese, yogurt, breast milk, and infant formula), etc.

Patients should be informed about what to do in the event they miss a dose of KALYDECO:

- In case a dose of KALYDECO is missed within 6 hours of the time it is usually taken, patients should be instructed to take the prescribed dose of KALYDECO with fat-containing food as soon as possible.
- If more than 6 hours have passed since KALYDECO is usually taken, the missed dose should NOT be taken, and the patient should resume the recommended dosing schedule.
- Patients should be advised to contact their healthcare provider if they have questions.

Cataracts

Inform patients that abnormality of the eye lens (cataract) has been noted in some children and adolescents receiving KALYDECO. Baseline and follow-up ophthalmological examinations should be performed in pediatric patients initiating KALYDECO treatment [see Warnings and Precautions (5.5)].

Manufactured for
Vertex Pharmaceuticals Incorporated
50 Northern Avenue
Boston, MA 02210

KALYDECO, VERTEX, and the VERTEX triangle logo are registered trademarks of Vertex Pharmaceuticals Incorporated.
All other trademarks referenced herein are the property of their respective owners.
©2025 Vertex Pharmaceuticals Incorporated
ALL RIGHTS RESERVED

Patient Information
KALYDECO® (kuh-LYE-deh-koh)
(ivacaftor) tablets, for oral use
(ivacaftor) oral granules

What is KALYDECO?

- KALYDECO is a prescription medicine used for the treatment of cystic fibrosis (CF) in people aged 1 month and older who have at least one mutation in the cystic fibrosis transmembrane conductance regulator (CFTR gene) that is responsive to KALYDECO.
- Talk to your doctor to learn if you have an indicated CF gene mutation.

It is not known if KALYDECO is safe and effective in children under 1 month of age.

Before taking KALYDECO, tell your doctor about all of your medical conditions, including if you:

- have liver or kidney problems.
- are allergic to KALYDECO or any ingredients in KALYDECO. See the end of this patient information leaflet for a complete list of ingredients in KALYDECO.
- are pregnant or plan to become pregnant. It is not known if KALYDECO will harm your unborn baby. You and your doctor should decide if you will take KALYDECO while you are pregnant.
- are breastfeeding or planning to breastfeed. It is not known if KALYDECO passes into your breast milk. You and your doctor should decide if you will take KALYDECO while you are breastfeeding.

Tell your doctor about all the medicines you take, including prescription and over-the-counter medicines, vitamins, and herbal supplements.
KALYDECO may affect the way other medicines work, and other medicines may affect how KALYDECO works. Ask your doctor or pharmacist for a list of these medicines if you are not sure.
Especially tell your doctor if you take:

- the antibiotics such as rifampin (RIFAMATE®, RIFATER®) or rifabutin (MYCOBUTIN®)
- seizure medicines such as phenobarbital, carbamazepine (TEGRETOL®, CARBATROL®, EQUETRO®) or phenytoin (DILANTIN®, PHENYTEK®)
- St. John's wort
- antifungal medicines such as ketoconazole, itraconazole (SPORANOX®), posaconazole (NOXAFIL®), voriconazole (VFEND®), or fluconazole (DIFLUCAN®)
- antibiotics such as telithromycin, clarithromycin (BIAXIN®), or erythromycin (ERY-TAB®)

Know the medicines you take. Keep a list of them to show your doctor and pharmacist when you get a new medicine.

How should I take KALYDECO?

- Take KALYDECO exactly as your doctor tells you to take it.
- Take your doses of KALYDECO 12 hours apart.
- Always take KALYDECO tablets or oral granules with food that contains fat. Examples of fat-containing foods include eggs, butter, peanut butter, cheese pizza, and whole-milk dairy products such as whole milk, cheese, yogurt, breast milk, or infant formula.
- KALYDECO Tablets (ages 6 years and older):
  - Each KALYDECO box contains 4 individual blister cards.
  - Each blister card contains 14 tablets: 7 morning doses and 7 evening doses.
  - In the morning, unpeel the paper backing from a blister card to remove 1 KALYDECO tablet and take it with food that contains fat.
  - In the evening, 12 hours later, open another blister card to remove 1 KALYDECO tablet and take it with food that contains fat.
  - Swallow the KALYDECO tablets whole.
  - You may cut along the dotted line to separate your doses from the blister card.
- KALYDECO Oral Granules (ages 1 month to under 6 years old):
  - Hold the packet with the cut line on top.
  - Shake the packet gently to settle the KALYDECO granules.
  - Tear or cut the packet open along the cut line.
  - Carefully pour all of the KALYDECO granules in the packet into 1 teaspoon of soft food or liquid. Food or liquid should be at or below room temperature. Some examples of soft foods or liquids include puréed fruits or vegetables, yogurt, applesauce, water, breast milk, infant formula, milk, or juice.
  - Mix the KALYDECO granules with soft food or liquid.
  - After mixing, give KALYDECO within 1 hour. Make sure all medicine is taken.
  - Give a child fat-containing food just before or just after the KALYDECO granules dose. Examples of fat-containing foods include eggs, butter, peanut butter, cheese pizza, and whole-milk dairy products such as whole milk, cheese, yogurt, breast milk and infant formula.
- If you miss a dose of KALYDECO and it is within 6 hours of when you usually take it, take your dose of KALYDECO as prescribed with fat-containing food as soon as possible.
- If you miss a dose of KALYDECO and it is more than 6 hours after the time you usually take it, skip that dose only and take the next dose when you usually take it. Do not take 2 doses at the same time to make up for your missed dose.

What should I avoid while taking KALYDECO?

- KALYDECO can cause dizziness in some people who take it. If you experience dizziness, do not drive or operate machines until symptoms improve.
- You should avoid food or drink containing grapefruit while you are taking KALYDECO.

What are the possible side effects of KALYDECO?
KALYDECO can cause serious side effects, including:

- High liver enzymes in the blood, which have happened in people receiving KALYDECO. Your doctor will do blood tests to check your liver:
  - before you start KALYDECO
  - every 3 months during your first year of taking KALYDECO
  - every year while you are taking KALYDECO
  For people who have had high liver enzymes in the past, your doctor may do blood tests to check the liver more often. Call your doctor right away if you have any of the following symptoms of liver problems:
  - pain or discomfort in the upper right stomach (abdominal) area
  - yellowing of your skin or the white part of your eyes
  - loss of appetite
  - nausea or vomiting
  - dark, amber-colored urine
- Serious Allergic Reactions can happen to people who are treated with KALYDECO. Call your healthcare provider or go to the emergency room right away if you have any symptoms of an allergic reaction. Symptoms of an allergic reaction may include:
  - rash or hives
  - tightness of the chest or throat or difficulty breathing
  - light-headedness or dizziness
- Increased pressure around the brain (intracranial hypertension) has happened in people treated with medicines containing the same or similar ingredients as KALYDECO. If you experience an unusual headache, blurred vision, double vision, or vision loss, call your doctor right away.
- Abnormality of the eye lens (cataract), which has happened in some children and adolescents receiving KALYDECO. Your doctor should perform eye examinations before and during treatment with KALYDECO to look for cataracts.

The most common side effects of KALYDECO include:

- headache
- upper respiratory tract infection (common cold) including sore throat, nasal or sinus congestion, and runny nose
- stomach (abdominal) pain

- diarrhea
- rash
- nausea
- dizziness

Tell your doctor if you have any side effect that bothers you or that does not go away.
These are not all the possible side effects of KALYDECO. For more information, ask your doctor or pharmacist.
Call your doctor for medical advice about side effects. You may report side effects to FDA at 1-800-FDA-1088.

How should I store KALYDECO?

- Store KALYDECO at room temperature between 68°F to 77°F (20°C to 25°C).

Keep KALYDECO and all medicines out of the reach of children.

General information about the safe and effective use of KALYDECO.
Medicines are sometimes prescribed for purposes other than those listed in a Patient Information leaflet. Do not use KALYDECO for a condition for which it was not prescribed. Do not give KALYDECO to other people, even if they have the same symptoms that you have. It may harm them.
You can ask your pharmacist or doctor for information about KALYDECO that is written for health professionals.

What are the ingredients in KALYDECO?
Ivacaftor tablets:
Active ingredients: ivacaftor.
Inactive ingredients: colloidal silicon dioxide, croscarmellose sodium, hypromellose acetate succinate, lactose monohydrate, magnesium stearate, microcrystalline cellulose, and sodium lauryl sulfate.
The tablet film coat contains: carnauba wax, FD&C Blue #2, PEG 3350, polyvinyl alcohol, talc, and titanium dioxide.
The printing ink contains: ammonium hydroxide, iron oxide black, propylene glycol, and shellac.
Ivacaftor oral granules:
Active ingredients: ivacaftor.
Inactive ingredients: colloidal silicon dioxide, croscarmellose sodium, hypromellose acetate succinate, lactose monohydrate, magnesium stearate, mannitol, sucralose, and sodium lauryl sulfate.
Manufactured for: Vertex Pharmaceuticals Incorporated, 50 Northern Avenue, Boston, MA 02210
KALYDECO, VERTEX, and the VERTEX triangle logo are registered trademarks of Vertex Pharmaceuticals Incorporated.
All other trademarks referenced herein are the property of their respective owners.
©2025 Vertex Pharmaceuticals Incorporated
For more information, go to www.kalydeco.com or call 1-877-752-5933.

This Patient Information has been approved by the U.S. Food and Drug Administration.

Revised: 09/2025

PRINCIPAL DISPLAY PANEL - 150 mg Tablet Blister Card Carton

NDC 51167-200-01
Rx only

kalydeco®
(ivacaftor) tablets

150 mg per tablet

Carton contains
4 individual blister cards
of 14 tablets per card.

56 tablets

PRINCIPAL DISPLAY PANEL - 150 mg Tablet Bottle Carton

NDC 51167-200-02
Rx only

kalydeco™
(ivacaftor) tablets

150 mg

60 tablets

PRINCIPAL DISPLAY PANEL - 50 mg Granule Packet Carton

Rx only
NDC 51167-300-01

kalydeco®
(ivacaftor) oral granules

50 mg

56 packets
Each packet contains 50 mg ivacaftor

Carton contains: 4 individual wallets
with 14 packets per wallet

Lift here to open

PRINCIPAL DISPLAY PANEL - 75 mg Granule Packet Carton

Rx only
NDC 51167-400-01

kalydeco®
(ivacaftor) oral granules

75 mg

56 packets
Each packet contains 75 mg ivacaftor

Carton contains: 4 individual wallets
with 14 packets per wallet

Lift here to open

PRINCIPAL DISPLAY PANEL - 25 mg Granule Packet Carton

Rx only
NDC 51167-600-01

kalydeco®
(ivacaftor) oral granules

25 mg

56 packets
Each packet contains 25 mg ivacaftor

Carton contains: 4 individual wallets
with 14 packets per wallet

Lift here to open

PRINCIPAL DISPLAY PANEL - 13.4 mg Granule Packet Carton

Rx only
NDC 51167-770-01

kalydeco®
(ivacaftor) oral granules

13.4 mg

56 packets
Each packet contains 13.4 mg ivacaftor

Carton contains: 4 individual wallets
with 14 packets per wallet

Lift here to open

PRINCIPAL DISPLAY PANEL - 5.8 mg Granule Packet Carton

Rx only
NDC 51167-785-01

kalydeco®
(ivacaftor) oral granules

5.8 mg

56 packets
Each packet contains 5.8 mg ivacaftor

Carton contains: 4 individual wallets
with 14 packets per wallet

Lift here to open